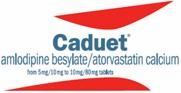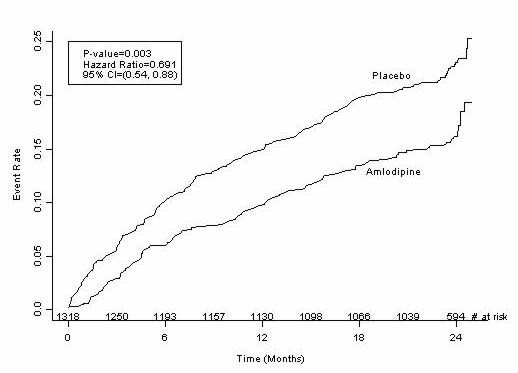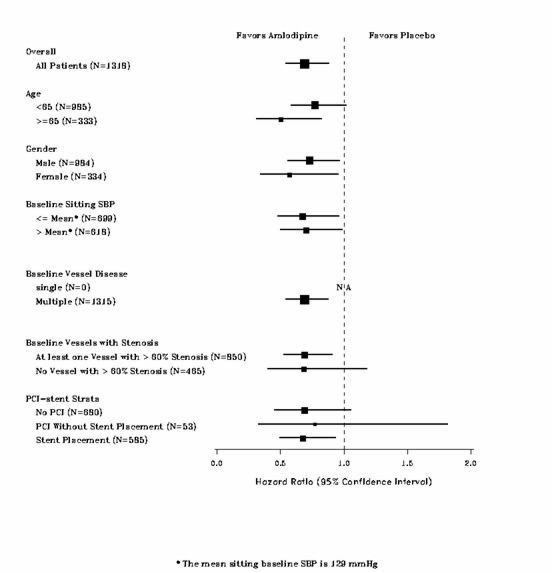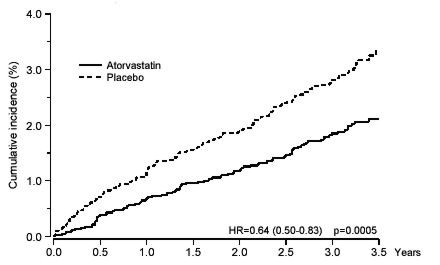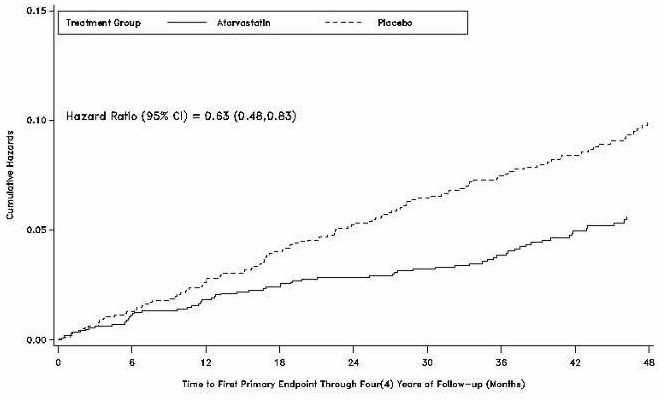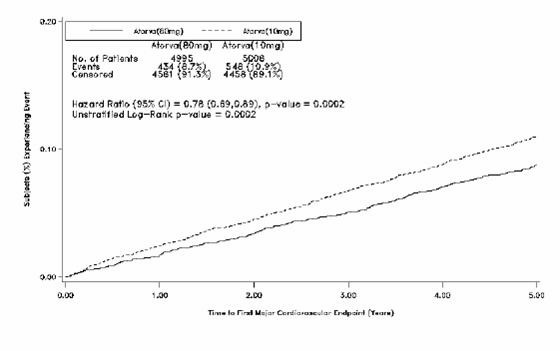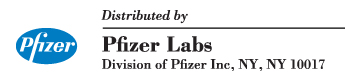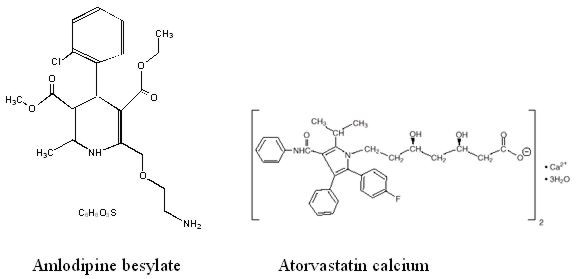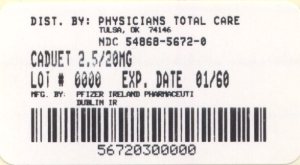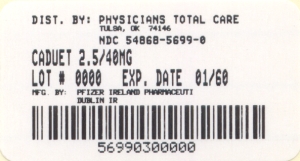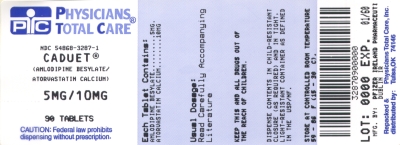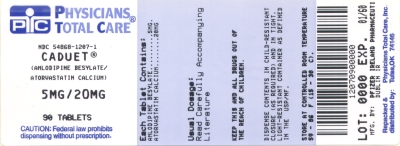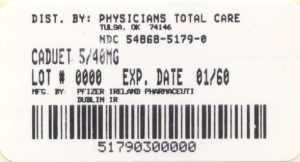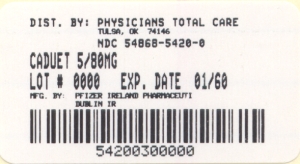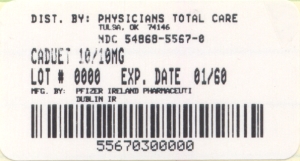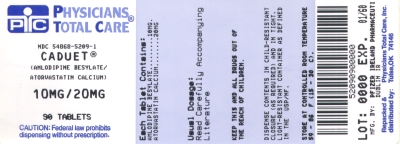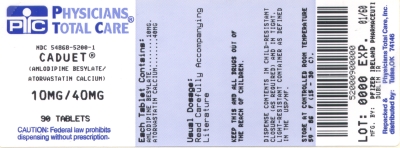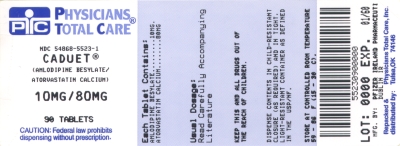 DRUG LABEL: Caduet
NDC: 54868-5672 | Form: TABLET, FILM COATED
Manufacturer: Physicians Total Care, Inc.
Category: prescription | Type: HUMAN PRESCRIPTION DRUG LABEL
Date: 20091130

ACTIVE INGREDIENTS: AMLODIPINE BESYLATE 2.5 mg/1 1; ATORVASTATIN CALCIUM 20 mg/1 1
INACTIVE INGREDIENTS: CALCIUM CARBONATE; CROSCARMELLOSE SODIUM; CELLULOSE, MICROCRYSTALLINE; POLYSORBATE 80; HYDROXYPROPYL CELLULOSE; WATER; SILICON DIOXIDE; MAGNESIUM STEARATE; POLYVINYL ALCOHOL; TITANIUM DIOXIDE; POLYETHYLENE GLYCOL 3000; TALC

DESCRIPTION

CADUET® (amlodipine besylate and atorvastatin calcium) tablets combine the calcium channel blocker amlodipine besylate with the lipid-lowering agent atorvastatin calcium.

The amlodipine besylate component of CADUET is chemically described as 3-ethyl-5-methyl (±)-2-[(2-aminoethoxy)methyl]-4-(o-chlorophenyl)-1,4-dihydro-6-methyl-3,5-pyridinedicarboxylate, monobenzenesulphonate. Its empirical formula is C20H25ClN2O5•C6H6O3S.

The atorvastatin calcium component of CADUET is chemically described as [R-(R*, R*)]-2-(4-fluorophenyl)-β, δ-dihydroxy-5-(1-methylethyl)-3-phenyl-4-[(phenylamino)carbonyl]-1H-pyrrole-1-heptanoic acid, calcium salt (2:1) trihydrate. Its empirical formula is (C33H34FN2O5)2Ca•3H2O.

The structural formulae for amlodipine besylate and atorvastatin calcium are shown below.

CADUET contains amlodipine besylate, a white to off-white crystalline powder, and atorvastatin calcium, also a white to off-white crystalline powder. Amlodipine besylate has a molecular weight of 567.1 and atorvastatin calcium has a molecular weight of 1209.42. Amlodipine besylate is slightly soluble in water and sparingly soluble in ethanol. Atorvastatin calcium is insoluble in aqueous solutions of pH 4 and below. Atorvastatin calcium is very slightly soluble in distilled water, pH 7.4 phosphate buffer, and acetonitrile; slightly soluble in ethanol, and freely soluble in methanol.

CADUET tablets are formulated for oral administration in the following strength combinations:

Table 1. CADUET Tablet Strengths
 | 2.5 mg/ 10mg | 2.5 mg/ 20mg | 2.5 mg/ 40mg | 5 mg/10 mg | 5 mg/20 mg | 5 mg/40 mg | 5 mg/80 mg | 10 mg/ 10 mg | 10 mg/ 20 mg | 10 mg/ 40 mg | 10 mg/ 80 mg
amlodipine equivalent (mg) | 2.5 | 2.5 | 2.5 | 5 | 5 | 5 | 5 | 10 | 10 | 10 | 10
atorvastatin equivalent (mg) | 10 | 20 | 40 | 10 | 20 | 40 | 80 | 10 | 20 | 40 | 80

Each tablet also contains calcium carbonate, croscarmellose sodium, microcrystalline cellulose, pregelatinized starch, polysorbate 80, hydroxypropyl cellulose, purified water, colloidal silicon dioxide (anhydrous), magnesium stearate, Opadry® II White 85F28751 (polyvinyl alcohol, titanium dioxide, PEG 3000 and talc) or Opadry® II Blue 85F10919 (polyvinyl alcohol, titanium dioxide, PEG 3000, talc and FD&C blue #2). Combinations of atorvastatin with 2.5 mg and 5 mg amlodipine are film coated white, and combinations of atorvastatin with 10 mg amlodipine are film coated blue.

CLINICAL PHARMACOLOGY

Mechanism of Action CADUET

CADUET is a combination of two drugs, a dihydropyridine calcium channel blocker amlodipine and an HMG-CoA reductase inhibitor atorvastatin. The amlodipine component of CADUET inhibits the transmembrane influx of calcium ions into vascular smooth muscle and cardiac muscle. The atorvastatin component of CADUET is a selective, competitive inhibitor of HMG-CoA reductase (statin), the rate-limiting enzyme that converts 3-hydroxy-3-methylglutaryl-coenzyme A to mevalonate, a precursor of sterols, including cholesterol.

Amlodipine

Experimental data suggest that amlodipine binds to both dihydropyridine and nondihydropyridine binding sites. The contractile processes of cardiac muscle and vascular smooth muscle are dependent upon the movement of extracellular calcium ions into these cells through specific ion channels. Amlodipine inhibits calcium ion influx across cell membranes selectively, with a greater effect on vascular smooth muscle cells than on cardiac muscle cells. Negative inotropic effects can be detected in vitro but such effects have not been seen in intact animals at therapeutic doses. Serum calcium concentration is not affected by amlodipine.

Amlodipine is a peripheral arterial vasodilator that acts directly on vascular smooth muscle to cause a reduction in peripheral vascular resistance and reduction in blood pressure.

The precise mechanisms by which amlodipine relieves angina have not been fully delineated, but are thought to include the following:

Exertional Angina: In patients with exertional angina, amlodipine reduces the total peripheral resistance (afterload) against which the heart works and reduces the rate pressure product, and thus myocardial oxygen demand, at any given level of exercise.

Vasospastic Angina: Amlodipine has been demonstrated to block constriction and restore blood flow in coronary arteries and arterioles in response to calcium, potassium epinephrine, serotonin, and thromboxane A2 analog in experimental animal models and in human coronary vessels in vitro. This inhibition of coronary spasm is responsible for the effectiveness of amlodipine in vasospastic (Prinzmetal's or variant) angina.

Atorvastatin

Cholesterol and triglycerides circulate in the bloodstream as part of lipoprotein complexes. With ultracentrifugation, these complexes separate into HDL (high-density lipoprotein), IDL (intermediate-density lipoprotein), LDL (low-density lipoprotein), and VLDL (very-low-density lipoprotein) fractions. Triglycerides (TG) and cholesterol in the liver are incorporated into VLDL and released into the plasma for delivery to peripheral tissues. LDL is formed from VLDL and is catabolized primarily through the high-affinity LDL receptor.

Clinical and pathologic studies show that elevated plasma levels of total cholesterol (total-C), LDL-cholesterol (LDL-C), and apolipoprotein B (apo B) promote human atherosclerosis and are risk factors for developing cardiovascular disease, while increased levels of HDL-C are associated with a decreased cardiovascular risk.

Epidemiologic investigations have established that cardiovascular morbidity and mortality vary directly with the level of total-C and LDL-C, and inversely with the level of HDL-C.

In animal models, atorvastatin lowers plasma cholesterol and lipoprotein levels by inhibiting HMG-CoA reductase and cholesterol synthesis in the liver and by increasing the number of hepatic LDL receptors on the cell-surface to enhance uptake and catabolism of LDL; atorvastatin also reduces LDL production and the number of LDL particles.

Atorvastatin reduces total-C, LDL-C, and apo B in patients with homozygous and heterozygous familial hypercholesterolemia (FH), nonfamilial forms of hypercholesterolemia, and mixed dyslipidemia. Atorvastatin also reduces VLDL-C and TG and produces variable increases in HDL-C and apolipoprotein A-1. Atorvastatin reduces total-C, LDL-C, VLDL-C, apo B, TG, and non-HDL-C, and increases HDL-C in patients with isolated hypertriglyceridemia. Atorvastatin reduces intermediate density lipoprotein cholesterol (IDL-C) in patients with dysbetalipoproteinemia.

Like LDL, cholesterol-enriched triglyceride-rich lipoproteins, including VLDL, intermediate density lipoprotein (IDL), and remnants, can also promote atherosclerosis. Elevated plasma triglycerides are frequently found in a triad with low HDL-C levels and small LDL particles, as well as in association with non-lipid metabolic risk factors for coronary heart disease. As such, total plasma TG has not consistently been shown to be an independent risk factor for CHD. Furthermore, the independent effect of raising HDL or lowering TG on the risk of coronary and cardiovascular morbidity and mortality has not been determined.

Pharmacokinetics and Metabolism Absorption Studies with amlodipine

After oral administration of therapeutic doses of amlodipine alone, absorption produces peak plasma concentrations between 6 and 12 hours. Absolute bioavailability has been estimated to be between 64% and 90%.

Studies with atorvastatin

After oral administration alone, atorvastatin is rapidly absorbed; maximum plasma concentrations occur within 1 to 2 hours. Extent of absorption increases in proportion to atorvastatin dose. The absolute bioavailability of atorvastatin (parent drug) is approximately 14% and the systemic availability of HMG-CoA reductase inhibitory activity is approximately 30%. The low systemic availability is attributed to presystemic clearance in gastrointestinal mucosa and/or hepatic first-pass metabolism. Plasma atorvastatin concentrations are lower (approximately 30% for Cmax and AUC) following evening drug administration compared with morning. However, LDL-C reduction is the same regardless of the time of day of drug administration (see DOSAGE AND ADMINISTRATION).

Studies with CADUET

Following oral administration of CADUET peak plasma concentrations of amlodipine and atorvastatin are seen at 6 to 12 hours and 1 to 2 hours post dosing, respectively. The rate and extent of absorption (bioavailability) of amlodipine and atorvastatin from CADUET are not significantly different from the bioavailability of amlodipine and atorvastatin administered separately (see above).

The bioavailability of amlodipine from CADUET was not affected by food. Food decreases the rate and extent of absorption of atorvastatin from CADUET by approximately 32% and 11%, respectively, as it does with atorvastatin when given alone. LDL-C reduction is similar whether atorvastatin is given with or without food.

Distribution Studies with amlodipine

Ex vivo studies have shown that approximately 93% of the circulating amlodipine drug is bound to plasma proteins in hypertensive patients. Steady-state plasma levels of amlodipine are reached after 7 to 8 days of consecutive daily dosing.

Studies with atorvastatin

Mean volume of distribution of atorvastatin is approximately 381 liters. Atorvastatin is ≥98% bound to plasma proteins. A blood/plasma ratio of approximately 0.25 indicates poor drug penetration into red blood cells. Based on observations in rats, atorvastatin calcium is likely to be secreted in human milk (see CONTRAINDICATIONS, Pregnancy and Lactation, and PRECAUTIONS, Nursing Mothers).

Metabolism Studies with amlodipine

Amlodipine is extensively (about 90%) converted to inactive metabolites via hepatic metabolism.

Studies with atorvastatin

Atorvastatin is extensively metabolized to ortho- and parahydroxylated derivatives and various beta-oxidation products. In vitro inhibition of HMG-CoA reductase by ortho- and parahydroxylated metabolites is equivalent to that of atorvastatin. Approximately 70% of circulating inhibitory activity for HMG-CoA reductase is attributed to active metabolites. In vitro studies suggest the importance of atorvastatin metabolism by cytochrome P450 3A4, consistent with increased plasma concentrations of atorvastatin in humans following coadministration with erythromycin, a known inhibitor of this isozyme (see PRECAUTIONS, Drug Interactions). In animals, the ortho-hydroxy metabolite undergoes further glucuronidation.

Excretion Studies with amlodipine

Elimination from the plasma is biphasic with a terminal elimination half-life of about 30–50 hours. Ten percent of the parent amlodipine compound and 60% of the metabolites of amlodipine are excreted in the urine.

Studies with atorvastatin

Atorvastatin and its metabolites are eliminated primarily in bile following hepatic and/or extra-hepatic metabolism; however, the drug does not appear to undergo enterohepatic recirculation. Mean plasma elimination half-life of atorvastatin in humans is approximately 14 hours, but the half-life of inhibitory activity for HMG-CoA reductase is 20 to 30 hours due to the contribution of active metabolites. Less than 2% of a dose of atorvastatin is recovered in urine following oral administration.

Specific Populations Geriatric Studies with amlodipine

Elderly patients have decreased clearance of amlodipine with a resulting increase in AUC of approximately 40–60%, and a lower initial dose of amlodipine may be required.

Studies with atorvastatin

Plasma concentrations of atorvastatin are higher (approximately 40% for Cmax and 30% for AUC) in healthy elderly subjects (age ≥65 years) than in young adults. Clinical data suggest a greater degree of LDL-lowering at any dose of atorvastatin in the elderly population compared to younger adults (see PRECAUTIONS, Geriatric Use).

Pediatric Studies with amlodipine

Sixty-two hypertensive patients aged 6 to 17 years received doses of amlodipine between 1.25 mg and 20 mg. Weight-adjusted clearance and volume of distribution were similar to values in adults.

Studies with atorvastatin

Pharmacokinetic data in the pediatric population are not available.

Gender Studies with atorvastatin

Plasma concentrations of atorvastatin in women differ from those in men (approximately 20% higher for Cmax and 10% lower for AUC); however, there is no clinically significant difference in LDL-C reduction with atorvastatin between men and women.

Renal Impairment Studies with amlodipine

The pharmacokinetics of amlodipine are not significantly influenced by renal impairment. Patients with renal failure may therefore receive the usual initial amlodipine dose.

Studies with atorvastatin

Renal disease has no influence on the plasma concentrations or LDL-C reduction of atorvastatin; thus, dose adjustment of atorvastatin in patients with renal dysfunction is not necessary (see DOSAGE AND ADMINISTRATION and WARNINGS, Skeletal Muscle).

Hemodialysis

While studies have not been conducted in patients with end-stage renal disease, hemodialysis is not expected to clear atorvastatin or amlodipine since both drugs are extensively bound to plasma proteins.

Hepatic Impairment

Atorvastatin is contraindicated in patients with active liver disease.

Studies with amlodipine

Elderly patients and patients with hepatic insufficiency have decreased clearance of amlodipine with a resulting increase in AUC of approximately 40–60%.

Studies with atorvastatin

In patients with chronic alcoholic liver disease, plasma concentrations of atorvastatin are markedly increased. Cmax and AUC are each 4-fold greater in patients with Childs-Pugh A disease. Cmax and AUC of atorvastatin are approximately 16-fold and 11-fold increased, respectively, in patients with Childs-Pugh B disease (see CONTRAINDICATIONS).

Heart Failure Studies with amlodipine

In patients with moderate to severe heart failure, the increase in AUC for amlodipine was similar to that seen in the elderly and in patients with hepatic insufficiency.

Pharmacokinetic Studies of Atorvastatin and Co-Administered Drugs

TABLE 2. Effect of Co-administered Drugs on the Pharmacokinetics of Atorvastatin
Co-administered drug and dosing regimen |  | Atorvastatin
 | Dose (mg) | Change in AUC* | Change in Cmax*
†Cyclosporine 5.2 mg/kg/day, stable dose | 10 mg QD for 28 days | ↑ 8.7-fold | ↑ 10.7-fold
†Lopinavir 400 mg BID/ ritonavir 100 mg BID, 14 days | 20 mg QD for 4 days | ↑ 5.9-fold | ↑ 4.7-fold
†Ritonavir 400 mg BID/ saquinavir 400mg BID, 15 days | 40 mg QD for 4 days | ↑ 3.9-fold | ↑ 4.3-fold
†Clarithromycin 500 mg BID, 9 days | 80 mg QD for 8 days | ↑ 4.4-fold | ↑ 5.4-fold
†Itraconazole 200 mg QD, 4 days | 40 mg SD | ↑ 3.3-fold | ↑ 20%
†Grapefruit Juice, 240 mL QD ‡ | 40 mg, SD | ↑ 37% | ↑ 16%
Diltiazem 240 mg QD, 28 days | 40 mg, SD | ↑ 51% | No change
Erythromycin 500 mg QID, 7 days | 10 mg, SD | ↑ 33% | ↑ 38%
Amlodipine 10 mg, single dose | 80 mg, SD | ↑ 15% | ↓ 12%
Cimetidine 300 mg QD, 4 weeks | 10 mg QD for 2 weeks | ↓ Less than 1% | ↓ 11%
Colestipol 10 mg BID, 28 weeks | 40 mg QD for 28 weeks | Not determined | ↓ 26%§
Maalox TC® 30 mL QD, 17 days | 10 mg QD for 15 days | ↓ 33% | ↓ 34%
Efavirenz 600 mg QD, 14 days | 10 mg for 3 days | ↓ 41% | ↓ 1%
†Rifampin 600 mg QD, 7 days (co-administered) ¶ | 40 mg SD | ↑ 30% | ↑ 2.7-fold
†Rifampin 600 mg QD, 5 days (doses separated) ¶ | 40 mg SD | ↓ 80% | ↓ 40%
†Gemfibrozil 600mg BID, 7 days | 40 mg SD | ↑ 35% | ↓ Less than 1%
†Fenofibrate 160mg QD, 7 days | 40 mg SD | ↑ 3% | ↑ 2%

* Data given as x-fold change represent a simple ratio between co-administration and atorvastatin alone (i.e., 1-fold = no change). Data given as % change represent % difference relative to atorvastatin alone (i.e., 0% = no change).
† See WARNINGS, Skeletal Muscle and PRECAUTIONS, Drug Interactions for clinical significance.
‡ Greater increases in AUC (up to 2.5-fold) and/or Cmax (up to 71%) have been reported with excessive grapefruit consumption (≥ 750 mL – 1.2 liters per day).
§ Single sample taken 8-16 h post dose.
¶ Due to the dual interaction mechanism of rifampin, simultaneous co-administration of atorvastatin with rifampin is recommended, as delayed administration of atorvastatin after administration of rifampin has been associated with a significant reduction in atorvastatin plasma concentrations.

TABLE 3. Effect of Atorvastatin on the Pharmacokinetics of Co-administered Drugs
Atorvastatin | Co-administered | drug and dosing regimen
 | Drug/Dose (mg) | Change in AUC | Change in Cmax
80 mg QD for 15 days | Antipyrine, 600 mg SD | ↑ 3% | ↓ 11%
80 mg QD for 14 days | * Digoxin 0.25 mg QD, 20 days | ↑ 15% | ↑ 20%
40 mg QD for 22 days | Oral contraceptive QD, 2 months
 | - norethindrone 1 mg | ↑ 28% | ↑ 23%
 | - ethinyl estradiol 35µg | ↑ 19% | ↑ 30%

* See PRECAUTIONS, Drug Interactions for clinical significance.
Pharmacodynamics Hemodynamic Effects of Amlodipine

Following administration of therapeutic doses to patients with hypertension, amlodipine produces vasodilation resulting in a reduction of supine and standing blood pressures. These decreases in blood pressure are not accompanied by a significant change in heart rate or plasma catecholamine levels with chronic dosing. Although the acute intravenous administration of amlodipine decreases arterial blood pressure and increases heart rate in hemodynamic studies of patients with chronic stable angina, chronic administration of oral amlodipine in clinical trials did not lead to clinically significant changes in heart rate or blood pressures in normotensive patients with angina.

With chronic once daily oral administration of amlodipine, antihypertensive effectiveness is maintained for at least 24 hours. Plasma concentrations correlate with effect in both young and elderly patients. The magnitude of reduction in blood pressure with amlodipine is also correlated with the height of pretreatment elevation; thus, individuals with moderate hypertension (diastolic pressure 105–114 mmHg) had about a 50% greater response than patients with mild hypertension (diastolic pressure 90–104 mmHg). Normotensive subjects experienced no clinically significant change in blood pressures (+1/–2 mmHg).

In hypertensive patients with normal renal function, therapeutic doses of amlodipine resulted in a decrease in renal vascular resistance and an increase in glomerular filtration rate and effective renal plasma flow without change in filtration fraction or proteinuria.

As with other calcium channel blockers, hemodynamic measurements of cardiac function at rest and during exercise (or pacing) in patients with normal ventricular function treated with amlodipine have generally demonstrated a small increase in cardiac index without significant influence on dP/dt or on left ventricular end diastolic pressure or volume. In hemodynamic studies, amlodipine has not been associated with a negative inotropic effect when administered in the therapeutic dose range to intact animals and man, even when co-administered with beta-blockers to man. Similar findings, however, have been observed in normals or well-compensated patients with heart failure with agents possessing significant negative inotropic effects.

Electrophysiologic Effects of Amlodipine

Amlodipine does not change sinoatrial nodal function or atrioventricular conduction in intact animals or man. In patients with chronic stable angina, intravenous administration of 10 mg did not significantly alter A-H and H-V conduction and sinus node recovery time after pacing. Similar results were obtained in patients receiving amlodipine and concomitant beta blockers. In clinical studies in which amlodipine was administered in combination with beta-blockers to patients with either hypertension or angina, no adverse effects on electrocardiographic parameters were observed. In clinical trials with angina patients alone, amlodipine therapy did not alter electrocardiographic intervals or produce higher degrees of AV blocks.

LDL-C Reduction with Atorvastatin

Atorvastatin as well as some of its metabolites are pharmacologically active in humans. The liver is the primary site of action and the principal site of cholesterol synthesis and LDL clearance. Drug dosage, rather than systemic drug concentration, correlates better with LDL-C reduction. Individualization of drug dosage should be based on therapeutic response (see DOSAGE AND ADMINISTRATION).

Clinical Studies Clinical Studies with Amlodipine Amlodipine Effects in Hypertension Adult Patients

The antihypertensive efficacy of amlodipine has been demonstrated in a total of 15 double-blind, placebo-controlled, randomized studies involving 800 patients on amlodipine and 538 on placebo. Once daily administration produced statistically significant placebo-corrected reductions in supine and standing blood pressures at 24 hours postdose, averaging about 12/6 mmHg in the standing position and 13/7 mmHg in the supine position in patients with mild to moderate hypertension. Maintenance of the blood pressure effect over the 24-hour dosing interval was observed, with little difference in peak and trough effect. Tolerance was not demonstrated in patients studied for up to 1 year. The 3 parallel, fixed doses, dose response studies showed that the reduction in supine and standing blood pressures was dose-related within the recommended dosing range. Effects on diastolic pressure were similar in young and older patients. The effect on systolic pressure was greater in older patients, perhaps because of greater baseline systolic pressure. Effects were similar in black patients and in white patients.

Pediatric Patients

Two-hundred sixty-eight hypertensive patients aged 6 to 17 years were randomized first to amlodipine 2.5 or 5 mg once daily for 4 weeks and then randomized again to the same dose or to placebo for another 4 weeks. Patients receiving 5 mg amlodipine at the end of 8 weeks had lower blood pressure than those secondarily randomized to placebo. The magnitude of the treatment effect is difficult to interpret, but it is probably less than 5 mmHg systolic on the 5 mg dose. Adverse events were similar to those seen in adults.

Amlodipine Effects in Chronic Stable Angina

The effectiveness of 5–10 mg/day of amlodipine in exercise-induced angina has been evaluated in 8 placebo-controlled, double-blind clinical trials of up to 6 weeks duration involving 1038 patients (684 amlodipine, 354 placebo) with chronic stable angina. In 5 of the 8 studies, significant increases in exercise time (bicycle or treadmill) were seen with the 10 mg dose. Increases in symptom-limited exercise time averaged 12.8% (63 sec) for amlodipine 10 mg, and averaged 7.9% (38 sec) for amlodipine 5 mg. Amlodipine 10 mg also increased time to 1 mm ST segment deviation in several studies and decreased angina attack rate. The sustained efficacy of amlodipine in angina patients has been demonstrated over long-term dosing. In patients with angina, there were no clinically significant reductions in blood pressures (4/1 mmHg) or changes in heart rate (+0.3 bpm).

Amlodipine Effects in Vasospastic Angina

In a double-blind, placebo-controlled clinical trial of 4 weeks duration in 50 patients, amlodipine therapy decreased attacks by approximately 4/week compared with a placebo decrease of approximately 1/week (p less than 0.01). Two of 23 amlodipine and 7 of 27 placebo patients discontinued from the study due to lack of clinical improvement.

Amlodipine Effects in Documented Coronary Artery Disease

In PREVENT, 825 patients with angiographically documented coronary artery disease were randomized to amlodipine (5–10 mg once daily) or placebo and followed for 3 years. Although the study did not show significance on the primary objective of change in coronary luminal diameter as assessed by quantitative coronary angiography, the data suggested a favorable outcome with respect to fewer hospitalizations for angina and revascularization procedures in patients with CAD.

CAMELOT enrolled 1318 patients with CAD recently documented by angiography, without left main coronary disease and without heart failure or an ejection fraction less than 40%. Patients (76% males, 89% Caucasian, 93% enrolled at US sites, 89% with a history of angina, 52% without PCI, 4% with PCI and no stent, and 44% with a stent) were randomized to double-blind treatment with either amlodipine (5 – 10 mg once daily) or placebo in addition to standard care that included aspirin (89%), statins (83%), beta-blockers (74%), nitroglycerin (50%), anti-coagulants (40%), and diuretics (32%), but excluded other calcium channel blockers. The mean duration of follow-up was 19 months. The primary endpoint was the time to first occurrence of one of the following events: hospitalization for angina pectoris, coronary revascularization, myocardial infarction, cardiovascular death, resuscitated cardiac arrest, hospitalization for heart failure, stroke/TIA, or peripheral vascular disease. A total of 110 (16.6%) and 151 (23.1%) first events occurred in the amlodipine and placebo groups respectively for a hazard ratio of 0.691 (95% CI: 0.540–0.884, p= 0.003). The primary endpoint is summarized in Figure 1 below. The outcome of this study was largely derived from the prevention of hospitalizations for angina and the prevention of revascularization procedures (see Table 4). Effects in various subgroups are shown in Figure 2.

In a angiographic substudy (n=274) conducted within CAMELOT, there was no significant difference between amlodipine and placebo on the change of atheroma volume in the coronary artery as assessed by intravascular ultrasound.

Figure 1: Kaplan-Meier analysis of composite clinical outcomes for amlodipine
versus placebo
Figure 2 – Effects on primary endpoint of amlodipine versus placebo across sub-groups
Table 4 below summarizes the significant composite endpoint and clinical outcomes from the composites of the primary endpoint. The other components of the primary endpoint including cardiovascular death, resuscitated cardiac arrest, myocardial infarction, hospitalization for heart failure, stroke/TIA, or peripheral vascular disease did not demonstrate a significant difference between amlodipine and placebo.

Table 4. Incidence of Significant Clinical Outcomes for CAMELOT
Clinical Outcomes N (%) | Amlodipine (N=663) | Placebo (N=655) | Risk Reduction (p-value)
Composite CV | 110 | 151 | 31%
Endpoint | (16.6) | (23.1) | (0.003)
Hospitalization for | 51 | 84 | 42%
Angina * | (7.7) | (12.8) | (0.002)
Coronary | 78 | 103 | 27%
Revascularization * | (11.8) | (15.7) | (0.033)

* Total patients with these events
Amlodipine Effects in Patients with Congestive Heart Failure

Amlodipine has been compared to placebo in four 8–12 week studies of patients with NYHA class II/III heart failure, involving a total of 697 patients. In these studies, there was no evidence of worsened heart failure based on measures of exercise tolerance, NYHA classification, symptoms, or LVEF. In a long-term (follow-up at least 6 months, mean 13.8 months) placebo-controlled mortality/morbidity study of amlodipine 5–10 mg in 1153 patients with NYHA classes III (n=931) or IV (n=222) heart failure on stable doses of diuretics, digoxin, and ACE inhibitors, amlodipine had no effect on the primary endpoint of the study which was the combined endpoint of all-cause mortality and cardiac morbidity (as defined by life-threatening arrhythmia, acute myocardial infarction, or hospitalization for worsened heart failure), or on NYHA classification, or symptoms of heart failure. Total combined all-cause mortality and cardiac morbidity events were 222/571 (39%) for patients on amlodipine and 246/583 (42%) for patients on placebo; the cardiac morbid events represented about 25% of the endpoints in the study.

Another study (PRAISE-2) randomized patients with NYHA class III (80%) or IV (20%) heart failure without clinical symptoms or objective evidence of underlying ischemic disease, on stable doses of ACE inhibitor (99%), digitalis (99%) and diuretics (99%), to placebo (n=827) or amlodipine (n=827) and followed them for a mean of 33 months. There was no statistically significant difference between amlodipine and placebo in the primary endpoint of all cause mortality (95% confidence limits from 8% reduction to 29% increase on amlodipine). With amlodipine there were more reports of pulmonary edema.

Clinical Studies with Atorvastatin Prevention of Cardiovascular Disease

In the Anglo-Scandinavian Cardiac Outcomes Trial (ASCOT), the effect of atorvastatin on fatal and non-fatal coronary heart disease was assessed in 10,305 hypertensive patients 40–80 years of age (mean of 63 years), without a previous myocardial infarction and with TC levels less than or equal to 251 mg/dl (6.5 mmol/l). Additionally all patients had at least 3 of the following cardiovascular risk factors: male gender (81.1%), age greater than 55 years (84.5%), smoking (33.2%), diabetes (24.3%), history of CHD in a first-degree relative (26%), TC:HDL greater than 6 (14.3%), peripheral vascular disease (5.1%), left ventricular hypertrophy (14.4%), prior cerebrovascular event (9.8%), specific ECG abnormality (14.3%), proteinuria/albuminuria (62.4%)]. In this double-blind, placebo-controlled study, patients were treated with anti-hypertensive therapy (Goal BP less than 140/90 mm Hg for non-diabetic patients; less than 130/80 mm Hg for diabetic patients) and allocated to either atorvastatin 10 mg daily (n=5168) or placebo (n=5137), using a covariate adaptive method which took into account the distribution of nine baseline characteristics of patients already enrolled and minimized the imbalance of those characteristics across the groups. Patients were followed for a median duration of 3.3 years.

The effect of 10 mg/day of atorvastatin on lipid levels was similar to that seen in previous clinical trials.

Atorvastatin significantly reduced the rate of coronary events [either fatal coronary heart disease (46 events in the placebo group vs. 40 events in the atorvastatin group) or nonfatal MI (108 events in the placebo group vs. 60 events in the atorvastatin group)] with a relative risk reduction of 36% [(based on incidences of 1.9% for atorvastatin vs. 3.0% for placebo), p=0.0005 (see Figure 3)]. The risk reduction was consistent regardless of age, smoking status, obesity, or presence of renal dysfunction. The effect of atorvastatin was seen regardless of baseline LDL levels. Due to the small number of events, results for women were inconclusive.

Figure 3: Effect of Atorvastatin 10 mg/day on Cumulative Incidence of Nonfatal
Myocardial Infarction or Coronary Heart Disease Death (in ASCOT-LLA)

Atorvastatin also significantly decreased the relative risk for revascularization procedures by 42%. Although the reduction of fatal and non-fatal strokes did not reach a pre-defined significance level (p 0.01), a favorable trend was observed with a 26% relative risk reduction (incidences of 1.7% for atorvastatin and 2.3% for placebo). There was no significant difference between the treatment groups for death due to cardiovascular causes (p=0.51) or noncardiovascular causes (p=0.17).

In the Collaborative Atorvastatin Diabetes Study (CARDS), the effect of atorvastatin on cardiovascular disease (CVD) endpoints was assessed in 2838 subjects (94% White, 68% male), ages 40–75 with type 2 diabetes based on WHO criteria, without prior history of cardiovascular disease and with LDL less than or equal to 160 mg/dL and TG less than or equal to 600 mg/dL. In addition to diabetes, subjects had 1 or more of the following risk factors: current smoking (23%), hypertension (80%), retinopathy (30%), or microalbuminuria (9%) or macroalbuminuria (3%). No subjects on hemodialysis were enrolled in the study. In this multicenter, placebo-controlled, double-blind clinical trial, subjects were randomly allocated to either atorvastatin 10 mg daily (1429) or placebo (1411) in a 1:1 ratio and were followed for a median duration of 3.9 years. The primary endpoint was the occurrence of any of the major cardiovascular events: myocardial infarction, acute CHD death, unstable angina, coronary revascularization, or stroke. The primary analysis was the time to first occurrence of the primary endpoint.

Baseline characteristics of subjects were: mean age of 62 years, mean HbA1c 7.7%; median LDL-C 120 mg/dL; median TC 207 mg/dL; median TG 151 mg/dL; median HDL-C 52 mg/dL.

The effect of atorvastatin 10 mg/day on lipid levels was similar to that seen in previous clinical trials.

Atorvastatin significantly reduced the rate of major cardiovascular events (primary endpoint events) (83 events in the atorvastatin group vs 127 events in the placebo group) with a relative risk reduction of 37%, HR 0.63, 95% CI (0.48,0.83) (p=0.001) (see Figure 4). An effect of atorvastatin was seen regardless of age, sex, or baseline lipid levels.

Figure 4. Effect of Atorvastatin 10 mg/day on Time to Occurrence of Major
Cardiovascular Events (myocardial infarction, acute CHD death, unstable angina,
coronary revascularization, or stroke) in CARDS.

Atorvastatin significantly reduced the risk of stroke by 48% (21 events in the atorvastatin group vs. 39 events in the placebo group), HR 0.52, 95% CI (0.31, 0.89) (p=0.016) and reduced the risk of MI by 42% (38 events in the atorvastatin group vs. 64 events in the placebo group), HR 0.58, 95.1% CI (0.39, 0.86) (p=0.007). There was no significant difference between the treatment groups for angina, revascularization procedures, and acute CHD death.

There were 61 deaths in the atorvastatin group vs. 82 deaths in the placebo group, (HR 0.73, p=0.059).

In the Treating to New Targets Study (TNT), the effect of LIPITOR 80 mg/day vs. LIPITOR 10 mg/day on the reduction in cardiovascular events was assessed in 10,001 subjects (94% white, 81% male, 38% greater than or equal to 65 years) with clinically evident coronary heart disease who had achieved a target LDL-C level less than 130 mg/dL after completing an 8-week, open-label, run-in period with LIPITOR 10 mg/day. Subjects were randomly assigned to either 10 mg/day or 80 mg/day of LIPITOR and followed for a median duration of 4.9 years. The primary endpoint was the time-to-first occurrence of any of the following major cardiovascular events (MCVE): death due to CHD, non-fatal myocardial infarction, resuscitated cardiac arrest, and fatal and non-fatal stroke. The mean LDL-C, TC, TG, non-HDL, and HDL cholesterol levels at 12 weeks were 73, 145, 128, 98, and 47 mg/dL during treatment with 80 mg of LIPITOR and 99, 177, 152, 129, and 48 mg/dL during treatment with 10 mg of LIPITOR.

Treatment with LIPITOR 80 mg/day significantly reduced the rate of MCVE (434 events in the 80mg/day group vs. 548 events in the 10 mg/day group) with a relative risk reduction of 22%, HR 0.78, 95% CI (0.69,0.89), p=0.0002 (see Figure5 and Table 5). The overall risk reduction was consistent regardless of age (less than 65, greate than or equal to 65) or gender.

Figure 5. Effect of LIPITOR 80 mg/day vs. 10 mg/day on Time to Occurrence of
Major Cardiovascular Events (TNT)

TABLE 5. Overview of Efficacy Results in TNT
Endpoint | Atorvastatin 10 mg (N=5006) |  | Atorvastatin 80 mg (N=4995) |  | HR* (95%CI)
PRIMARY ENDPOINT | n | (%) | n | (%)
First major cardiovascular endpoint | 548 | (10.9) | 434 | (8.7) | 0.78 (0.69, 0.89)
Components of the Primary Endpoint
CHD death | 127 | (2.5) | 101 | (2.0) | 0.80 (0.61, 103)
Non-fatal, non-procedure related MI | 308 | (6.2) | 243 | (4.9) | 0.78 (0.66, 0.93)
Resuscitated cardiac arrest | 26 | (0.5) | 25 | (0.5) | 0.96 (0.56, 1.67)
Stroke (fatal and non-fatal) | 155 | (3.1) | 117 | (2.3) | 0.75 (0.59, 0.96)
SECONDARY ENDPOINTS†
First CHF with hospitalization | 164 | (3.3) | 122 | (2.4) | 0.74 (0.59, 0.94)
First PVD endpoint | 282 | (5.6) | 275 | (5.5) | 0.97 (0.83, 1.15)
First CABG or other coronary revascularization procedure‡ | 904 | (18.1) | 667 | (13.4) | 0.72 (0.65, 0.80)
First documented angina endpoint‡ | 615 | 12.3) | 545 | (10.9) | 0.88 (0.79, 0.99)
All cause mortality | 282 | (5.6) | 284 | (5.7) | 1.01 (0.85, 1.19)
Components of all cause mortality
Cardiovascular death | 155 | (3.1) | 126 | (2.5) | 0.81 (0.64, 1.03)
Noncardiovascular death | 127 | (2.5) | 158 | (3.2) | 1.25 (0.99, 1.57)
Cancer death | 75 | (1.5) | 85 | (1.7) | 1.13 (0.83, 1.55)
Other non-CV death | 43 | (0.9) | 58 | (1.2) | 1.35 (0.91, 2.00)
Suicide, homicide and other traumatic non-CV death | 9 | (0.2) | 15 | (0.3) | 1.67 (0.73, 3.82)

HR=hazard ratio, CHD =coronary heart disease; CI=confidence interval; MI=myocardial infarction; CHF=congestive heart failure;
CV=cardiovascular; PVD=peripheral vascular disease; CABG=coronary artery bypass graft
Confidence intervals for the Secondary Endpoints were not adjusted for multiple comparisons.
* Atorvastatin 80 mg: atorvastatin 10 mg
† Secondary endpoints not included in primary endpoint
‡ Component of other secondary endpoints

Of the events that comprised the primary efficacy endpoint, treatment with LIPITOR 80 mg/day significantly reduced the rate of non-fatal, non-procedure related MI and fatal and non-fatal stroke, but not CHD death or resuscitated cardiac arrest (Table 5). Of the predefined secondary endpoints, treatment with LIPITOR 80 mg/day significantly reduced the rate of coronary revascularization, angina, and hospitalization for heart failure, but not peripheral vascular disease. The reduction in the rate of CHF with hospitalization was only observed in the 8% of patients with a prior history of CHF.

There was no significant difference between the treatment groups for all-cause mortality (Table 5). The proportions of subjects who experienced cardiovascular death, including the components of CHD death and fatal stroke, were numerically smaller in the LIPITOR 80 mg group than in the LIPITOR 10 mg treatment group. The proportions of subjects who experienced noncardiovascular death were numerically larger in the LIPITOR 80 mg group than in the LIPITOR 10 mg treatment group.

In the Incremental Decrease in Endpoints Through Aggressive Lipid Lowering Study (IDEAL), treatment with LIPITOR 80 mg/day was compared to treatment with simvastatin 20–40 mg/day in 8,888 subjects up to 80 years of age with a history of CHD to assess whether reduction in CV risk could be achieved. Patients were mainly male (81%), white (99%) with an average age of 61.7 years, and an average LDL-C of 121.5 mg/dL at randomization; 76% were on statin therapy. In this prospective, randomized, open-label, blinded endpoint (PROBE) trial with no run-in period, subjects were followed for a median duration of 4.8 years. The mean LDL-C, TC, TG, HDL, and non-HDL cholesterol levels at Week 12 were 78, 145, 115, 45, and 100 mg/dL during treatment with 80 mg of LIPITOR and 105, 179, 142, 47, and 132 mg/dL during treatment with 20–40 mg of simvastatin.

There was no significant difference between the treatment groups for the primary endpoint, the rate of first major coronary event (fatal CHD, nonfatal MI and resuscitated cardiac arrest): 411 (9.3%) in the LIPITOR 80 mg/day group vs. 463 (10.4%) in the simvastatin 20–40 mg/day group, HR 0.89, 95% CI (0.78, 1.01), p=0.07.

There were no significant differences between the treatment groups for all-cause mortality: 366 (8.2%) in the LIPITOR 80 mg/day group vs. 374 (8.4%) in the simvastatin 20–40 mg/day group. The proportions of subjects who experienced CV or non-CV death were similar for the LIPITOR 80 mg group and the simvastatin 20–40 mg group.

Atorvastatin Studies in Hyperlipidemia (Heterozygous Familial and Nonfamilial) and Mixed Dyslipidemia (Fredrickson Types IIa and IIb)

Atorvastatin reduces total-C, LDL-C, VLDL-C, apo B, and TG, and increases HDL-C in patients with hyperlipidemia and mixed dyslipidemia. Therapeutic response is seen within 2 weeks, and maximum response is usually achieved within 4 weeks and maintained during chronic therapy.

Atorvastatin is effective in a wide variety of patient populations with hyperlipidemia, with and without hypertriglyceridemia, in men and women, and in the elderly.

In two multicenter, placebo-controlled, dose-response studies in patients with hyperlipidemia, atorvastatin given as a single dose over 6 weeks, significantly reduced total-C, LDL-C, apo B, and TG (pooled results are provided in Table 6).

Table 6. Dose-Response in Patients With Primary Hyperlipidemia (Adjusted Mean Percent Change From Baseline)*
Dose | N | TC | LDL-C | Apo B | TG | HDL-C | Non-HDL-C/ HDL-C
Placebo | 21 | 4 | 4 | 3 | 10 | -3 | 7
10 | 22 | -29 | -39 | -32 | -19 | 6 | -34
20 | 20 | -33 | -43 | -35 | -26 | 9 | -41
40 | 21 | -37 | -50 | -42 | -29 | 6 | -45
80 | 23 | -45 | -60 | -50 | -37 | 5 | -53

* Results are pooled from 2 dose-response studies.

In patients with Fredrickson Types IIa and IIb hyperlipoproteinemia pooled from 24 controlled trials, the median (25th and 75th percentile) percent changes from baseline in HDL-C for atorvastatin 10, 20, 40, and 80 mg were 6.4 (-1.4, 14), 8.7 (0, 17), 7.8 (0, 16), and 5.1 (-2.7, 15), respectively. Additionally, analysis of the pooled data demonstrated consistent and significant decreases in total-C, LDL-C, TG, total-C/HDL-C, and LDL-C/HDL-C.

In three multicenter, double-blind studies in patients with hyperlipidemia, atorvastatin was compared to other statins. After randomization, patients were treated for 16 weeks with either atorvastatin 10 mg per day or a fixed dose of the comparative agent (Table 7).

Table 7. Mean Percent Change From Baseline at Endpoint (Double-Blind, Randomized, Active-Controlled Trials)
Treatment (Daily Dose) | N | Total-C | LDL-C | Apo B | TG | HDL-C | Non-HDL-C/ HDL-C
Study 1
Atorvastatin 10 mg | 707 | -27* | -36* | -28* | -17* | +7 | -37*
Lovastatin 20 mg | 191 | -19 | -27 | -20 | -6 | +7 | -28
95% CI for Diff† |  | -9.2, -6.5 | -10.7, -7.1 | -10.0, -6.5 | -15.2, -7.1 | -1.7, 2.0 | -11.1, -7.1
Study 2
Atorvastatin 10 mg | 222 | -25‡ | -35‡ | -27‡ | -17‡ | +6 | -36‡
Pravastatin 20 mg | 77 | -17 | -23 | -17 | -9 | +8 | -28
95% CI for Diff† |  | -10.8, -6.1 | -14.5, -8.2 | -13.4, -7.4 | -14.1, -0.7 | -4.9, 1.6 | -11.5, -4.1
Study 3
Atorvastatin 10 mg | 132 | -29§ | -37§ | -34§ | -23§ | +7 | -39§
Simvastatin 10 mg | 45 | -24 | -30 | -30 | -15 | +7 | -33
95% CI for Diff† |  | -8.7, -2.7 | -10.1, -2.6 | -8.0, -1.1 | -15.1, -0.7 | -4.3, 3.9 | -9.6, -1.9

* Significantly different from lovastatin, ANCOVA, p less than or equal to 0.05
† A negative value for the 95% CI for the difference between treatments favors atorvastatin for all except HDL-C, for which a positive value favors atorvastatin. If the range does not include 0, this indicates a statistically significant difference.
‡ Significantly different from pravastatin, ANCOVA, p less than or equal to 0.05
§
Significantly different from simvastatin, ANCOVA, p less than or equal to 0.05

The impact on clinical outcomes of the differences in lipid-altering effects between treatments shown in Table 7 is not known. Table 7 does not contain data comparing the effects of atorvastatin 10 mg and higher doses of lovastatin, pravastatin, and simvastatin. The drugs compared in the studies summarized in the table are not necessarily interchangeable.

Atorvastatin Effects in Hypertriglyceridemia (Fredrickson Type IV)

The response to atorvastatin in 64 patients with isolated hypertriglyceridemia treated across several clinical trials is shown in the table below (Table 8). For the atorvastatin-treated patients, median (min, max) baseline TG level was 565 (267–1502).

Table 8. Combined Patients With Isolated Elevated TG: Median (min, max) Percent Changes From Baseline
 | Placebo (N=12) | Atorvastatin 10 mg (N=37) | Atorvastatin 20 mg (N=13) | Atorvastatin 80 mg (N=14)
Triglycerides | -12.4 (-36.6, 82.7) | -41.0 (-76.2, 49.4) | -38.7 (-62.7, 29.5) | -51.8 (-82.8, 41.3)
Total-C | -2.3 (-15.5, 24.4) | -28.2 (-44.9, -6.8) | -34.9 (-49.6, -15.2) | -44.4 (-63.5, -3.8)
LDL-C | 3.6 (-31.3, 31.6) | -26.5 (-57.7, 9.8) | -30.4 (-53.9, 0.3) | -40.5 (-60.6, -13.8)
HDL-C | 3.8 (-18.6, 13.4) | 13.8 (-9.7, 61.5) | 11.0 (-3.2, 25.2) | 7.5 (-10.8, 37.2)
VLDL-C | -1.0 (-31.9, 53.2) | -48.8 (-85.8, 57.3) | -44.6 (-62.2, -10.8) | -62.0 (-88.2, 37.6)
non-HDL-C | -2.8 (-17.6, 30.0) | -33.0 (-52.1, -13.3) | -42.7 (-53.7, -17.4) | -51.5 (-72.9, -4.3)

Atorvastatin Effects in Dysbetalipoproteinemia (Fredrickson Type III)

The results of an open-label crossover study of atorvastatin in 16 patients (genotypes: 14 apo E2/E2 and 2 apo E3/E2) with dysbetalipoproteinemia (Fredrickson Type III) are shown in the table below (Table 9).

Table 9. Open-Label Crossover Study of 16 Patients With Dysbetalipoproteinemia (Fredrickson Type III)
 |  | Median % Change (min, max)
 | Median (min, max) at Baseline (mg/dL) | Atorvastatin 10 mg | Atorvastatin 80 mg
Total-C | 442 (225, 1320) | -37 (-85, 17) | -58 (-90, -31)
Triglycerides | 678 (273, 5990) | -39 (-92, -8) | -53 (-95, -30)
IDL-C + VLDL-C | 215 (111, 613) | -32 (-76, 9) | -63 (-90, -8)
non-HDL-C | 411 (218, 1272) | -43 (-87, -19) | -64 (-92, -36)

Atorvastatin Effects in Homozygous Familial Hypercholesterolemia

In a study without a concurrent control group, 29 patients ages 6 to 37 years with homozygous FH received maximum daily doses of 20 to 80 mg of atorvastatin. The mean LDL-C reduction in this study was 18%. Twenty-five patients with a reduction in LDL-C had a mean response of 20% (range of 7% to 53%, median of 24%); the remaining 4 patients had 7% to 24% increases in LDL-C. Five of the 29 patients had absent LDL-receptor function. Of these, 2 patients also had a portacaval shunt and had no significant reduction in LDL-C. The remaining 3 receptor-negative patients had a mean LDL-C reduction of 22%.

Atorvastatin Effects in Heterozygous Familial Hypercholesterolemic Pediatric Patients

In a double-blind, placebo-controlled study followed by an open-label phase, 187 boys and postmenarchal girls 10–17 years of age (mean age 14.1 years) with heterozygous FH or severe hypercholesterolemia, were randomized to atorvastatin (n=140) or placebo (n=47) for 26 weeks and then all received atorvastatin for 26 weeks. Inclusion in the study required 1) a baseline LDL-C level ≥ 190 mg/dL or 2) a baseline LDL-C level ≥ 160 mg/dL and positive family history of FH or documented premature cardiovascular disease in a first- or second-degree relative. The mean baseline LDL-C value was 218.6 mg/dL (range: 138.5–385.0 mg/dL) in the atorvastatin group compared to 230.0 mg/dL (range: 160.0–324.5 mg/dL) in placebo group. The dosage of atorvastatin (once daily) was 10 mg for the first 4 weeks and up-titrated to 20 mg if the LDL-C level was > 130 mg/dL. The number of atorvastatin-treated patients who required up-titration to 20 mg after Week 4 during the double-blind phase was 80 (57.1%).

Atorvastatin significantly decreased plasma levels of total-C, LDL-C, triglycerides, and apolipoprotein B during the 26 week double-blind phase (see Table 10).

Table 10. Lipid-altering Effects of Atorvastatin in Adolescent Boys and Girls with Heterozygous Familial Hypercholesterolemia or Severe Hypercholesterolemia (Mean Percent Change From Baseline at Endpoint in Intention-to-Treat Population)
DOSAGE | N | Total-C | LDL-C | HDL-C | TG | Apolipoprotein B
Placebo | 47 | -1.5 | -0.4 | -1.9 | 1.0 | 0.7
Atorvastatin | 140 | -31.4 | -39.6 | 2.8 | -12.0 | -34.0

The mean achieved LDL-C value was 130.7 mg/dL (range: 70.0–242.0 mg/dL) in the atorvastatin group compared to 228.5 mg/dL (range: 152.0–385.0 mg/dL) in the placebo group during the 26 week double-blind phase.

The safety and efficacy of atorvastatin doses above 20 mg have not been studied in controlled trials in children. The long-term efficacy of atorvastatin therapy in childhood to reduce morbidity and mortality in adulthood has not been established.

Clinical Study of Combined Amlodipine and Atorvastatin in Patients with Hypertension and Dyslipidemia

In a double-blind, placebo-controlled study, a total of 1660 patients with co-morbid hypertension and dyslipidemia received once daily treatment with eight dose combinations of amlodipine and atorvastatin (5/10, 10/10, 5/20, 10/20, 5/40, 10/40, 5/80, or 10/80 mg), amlodipine alone (5 mg or 10 mg), atorvastatin alone (10 mg, 20 mg, 40 mg, or 80 mg) or placebo. In addition to concomitant hypertension and dyslipidemia, 15% of the patients had diabetes mellitus, 22% were smokers and 14% had a positive family history of cardiovascular disease. At eight weeks, all eight combination-treatment groups of amlodipine and atorvastatin demonstrated statistically significant dose-related reductions in systolic blood pressure (SBP), diastolic blood pressure (DBP) and LDL-C compared to placebo, with no overall modification of effect of either component on SBP, DBP and LDL-C (Table 11).

Table 11. Efficacy in Terms of Reduction in Blood Pressure and LDL-C
Efficacy of the Combined Treatments in Reducing Systolic BP
Parameter / Analysis | ATO 0 mg | ATO 10 mg | ATO 20 mg | ATO 40 mg | ATO 80 mg
 | Mean change (mmHg) | -3.0 | -4.5 | -6.2 | -6.2 | -6.4
AML 0 mg
 | Difference versus placebo (mmHg) | - | -1.5 | -3.2 | -3.2 | -3.4
 | Mean change (mmHg) | -12.8 | -13.7 | -15.3 | -12.7 | -12.2
AML 5 mg
 | Difference versus placebo (mmHg) | -9.8 | -10.7 | -12.3 | -9.7 | -9.2
 | Mean change (mmHg) | -16.2 | -15.9 | -16.1 | -16.3 | -17.6
AML 10 mg
 | Difference versus placebo (mmHg) | -13.2 | -12.9 | -13.1 | -13.3 | -14.6
Efficacy of the Combined Treatments in Reducing Diastolic BP
Parameter / Analysis | ATO 0 mg | ATO 10 mg | ATO 20 mg | ATO 40 mg | ATO 80 mg
 | Mean change (mmHg) | -3.3 | -4.1 | -3.9 | -5.1 | -4.1
AML 0 mg
 | Difference versus placebo (mmHg) | - | -0.8 | -0.6 | -1.8 | -0.8
 | Mean change (mmHg) | -7.6 | -8.2 | -9.4 | -7.3 | -8.4
AML 5 mg
 | Difference versus placebo (mmHg) | -4.3 | -4.9 | -6.1 | -4.0 | -5.1
 | Mean change (mmHg) | -10.4 | -9.1 | -10.6 | -9.8 | -11.1
AML 10 mg
 | Difference versus placebo (mmHg) | -7.1 | -5.8 | -7.3 | -6.5 | -7.8
Efficacy of the Combined Treatments in Reducing LDL-C (% change)
Parameter / Analysis | ATO 0 mg | ATO 10 mg | ATO 20 mg | ATO 40 mg | ATO 80 mg
AML 0 mg | Mean % change | -1.1 | -33.4 | -39.5 | -43.1 | -47.2
AML 5 mg | Mean % change | -0.1 | -38.7 | -42.3 | -44.9 | -48.4
AML 10 mg | Mean % change | -2.5 | -36.6 | -38.6 | -43.2 | -49.1

INDICATIONS AND USAGE

CADUET (amlodipine and atorvastatin) is indicated in patients for whom treatment with both amlodipine and atorvastatin is appropriate.

Amlodipine1. Hypertension: Amlodipine is indicated for the treatment of hypertension. It may be used alone or in combination with other antihypertensive agents; 2. Coronary Artery Disease (CAD)
Chronic Stable Angina: Amlodipine is indicated for the treatment of chronic stable angina. Amlodipine may be used alone or in combination with other antianginal or antihypertensive agents;
Vasospastic Angina (Prinzmetal's or Variant Angina): Amlodipine is indicated for the treatment of confirmed or suspected vasospastic angina. Amlodipine may be used as monotherapy or in combination with other antianginal drugs.
Angiographically Documented CAD: In patients with recently documented CAD by angiography and without heart failure or an ejection fraction less than 40%, amlodipine is indicated to reduce the risk of hospitalization due to angina and to reduce the risk of a coronary revascularization procedure.

AND

Atorvastatin

Therapy with lipid-altering agents should be only one component of multiple risk factor intervention in individuals at significantly increased risk for atherosclerotic vascular disease due to hypercholesterolemia. Drug therapy is recommended as an adjunct to diet when the response to a diet restricted in saturated fat and cholesterol and other nonpharmacologic measures alone has been inadequate. In patients with CHD or multiple risk factors for CHD, the atorvastatin component of CADUET can be started simultaneously with diet restriction.

1. Prevention of Cardiovascular Disease: In adult patients without clinically evident coronary heart disease, but with multiple risk factors for coronary heart disease such as age, smoking, hypertension, low HDL-C, or a family history of early coronary heart disease, atorvastatin is indicated to:

- Reduce the risk of myocardial infarction
- Reduce the risk of stroke
- Reduce the risk for revascularization procedures and angina

In patients with type 2 diabetes, and without clinically evident coronary heart disease, but with multiple risk factors for coronary heart disease such as retinopathy, albuminuria, smoking, or hypertension, LIPITOR is indicated to:

- Reduce the risk of myocardial infarction
- Reduce the risk of stroke;

In patients with clinically evident coronary heart disease, LIPITOR is indicated to:

- Reduce the risk of non-fatal myocardial infarction
- Reduce the risk of fatal and non-fatal stroke
- Reduce the risk for revascularization procedures
- Reduce the risk of hospitalization for CHF
- Reduce the risk of angina

2. Heterozygous Familial and Nonfamilial Hyperlipidemia: Atorvastatin is indicated as an adjunct to diet to reduce elevated total-C, LDL-C, apo B, and TG levels and to increase HDL-C in patients with primary hypercholesterolemia (heterozygous familial and nonfamilial) and mixed dyslipidemia (Fredrickson Types IIa and IIb); 3. Elevated Serum TG Levels: Atorvastatin is indicated as an adjunct to diet for the treatment of patients with elevated serum TG levels (Fredrickson Type IV); 4. Primary Dysbetalipoproteinemia: Atorvastatin is indicated for the treatment of patients with primary dysbetalipoproteinemia (Fredrickson Type III) who do not respond adequately to diet; 5. Homozygous Familial Hypercholesterolemia: Atorvastatin is indicated to reduce total-C and LDL-C in patients with homozygous familial hypercholesterolemia as an adjunct to other lipid-lowering treatments (e.g., LDL apheresis) or if such treatments are unavailable; 6. Pediatric Patients: Atorvastatin is indicated as an adjunct to diet to reduce total-C, LDL-C, and apo B levels in boys and postmenarchal girls, 10 to 17 years of age, with heterozygous familial hypercholesterolemia if after an adequate trial of diet therapy the following findings are present:

1. LDL-C remains greater than or equal to 190 mg/dL or
2. LDL-C remains greater than or equal to 160 mg/dL and:
  - there is a positive family history of premature cardiovascular disease or
  - two or more other CVD risk factors are present in the pediatric patients.

The antidyslipidemic component of CADUET has not been studied in conditions where the major lipoprotein abnormality is elevation of chylomicrons (Fredrickson Types I and V).

CONTRAINDICATIONS

CADUET contains atorvastatin and is therefore contraindicated in patients with active liver disease, which may include unexplained persistent elevations in hepatic transaminase levels.

CADUET is contraindicated in patients with known hypersensitivity to any component of this medication.

Pregnancy and Lactation

CADUET contains atorvastatin and is therefore contraindicated in women who are pregnant or may become pregnant. The atorvastatin component of CADUET may cause fetal harm when administered to a pregnant woman. Serum cholesterol and triglycerides increase during normal pregnancy, and cholesterol or cholesterol derivatives are essential for fetal development. Atherosclerosis is a chronic process and discontinuation of lipid-lowering drugs during pregnancy should have little impact on the outcome of long-term therapy of primary hypercholesterolemia.

There are no adequate and well-controlled studies of atorvastatin use during pregnancy; however in rare reports congenital anomalies were observed following intrauterine exposure to statins. In rat and rabbit animal reproduction studies, atorvastatin revealed no evidence of teratogenicity. CADUET, WHICH INCLUDES ATORVASTATIN, SHOULD BE ADMINISTERED TO WOMEN OF CHILDBEARING AGE ONLY WHEN SUCH PATIENTS ARE HIGHLY UNLIKELY TO CONCEIVE AND HAVE BEEN INFORMED OF THE POTENTIAL HAZARDS. If the patient becomes pregnant while taking this drug, therapy should be discontinued immediately and the patient apprised of the potential hazard to the fetus (see PRECAUTIONS, Pregnancy).

It is not known whether atorvastatin or amlodipine are excreted into human milk; however a small amount of another statin does pass into breast milk. Because statins have the potential for serious adverse reactions in nursing infants, women taking CADUET should not breastfeed their infants (see PRECAUTIONS, Nursing Mothers).

WARNINGS

Skeletal Muscle

Rare cases of rhabdomyolysis with acute renal failure secondary to myoglobinuria have been reported with the atorvastatin component of CADUET and with other statins. A history of renal impairment may be a risk factor for the development of rhabdomyolysis. Such patients merit closer monitoring for skeletal muscle effects.

The atorvastatin component of CADUET, like other statins, occasionally causes myopathy, defined as muscle aches or muscle weakness in conjunction with increases in creatine phosphokinase (CPK) values >10 times ULN. The concomitant use of higher doses of atorvastatin with certain drugs such as cyclosporine and strong CYP3A4 inhibitors (e.g., clarithromycin, itraconazole and HIV protease inhibitors) increases the risk of myopathy/rhabdomyolysis.

Myopathy should be considered in any patient with diffuse myalgias, muscle tenderness or weakness, or marked elevation of CPK. Patients should be advised to report promptly unexplained muscle pain, tenderness or weakness, particularly if accompanied by malaise or fever. CADUET therapy should be discontinued if markedly elevated CPK levels occur or myopathy is diagnosed or suspected.

The risk of myopathy during treatment with statins is increased with concurrent administration of cyclosporine, fibric acid derivatives, erythromycin, clarithromycin, combination of ritonavir plus saquinavir or lopinavir plus ritonavir, niacin, or azole antifungals. Physicians considering combined therapy with CADUET and fibric acid derivatives, erythromycin, clarithromycin, a combination of ritonavir plus saquinavir or lopinavir plus ritonavir, immunosuppressive drugs, azole antifungals, or lipid-modifying doses of niacin should carefully weigh the potential benefits and risks and should carefully monitor patients for any signs or symptoms of muscle pain, tenderness, or weakness, particularly during the initial months of therapy and during any periods of upward dosage titration of either drug. Lower starting and maintenance doses of atorvastatin should be considered when taken concomitantly with the aforementioned drugs (see PRECAUTIONS, Drug Interactions). Periodic creatine phosphokinase (CPK) determinations may be considered in such situations, but there is no assurance that such monitoring will prevent the occurrence of severe myopathy.

Prescribing recommendations for atorvastatin, a component of CADUET, and interacting agents are summarized in Table 12 (see DOSAGE AND ADMINISTRATION, PRECAUTIONS, Drug Interactions, and CLINICAL PHARMACOLOGY).

TABLE 12 Atorvastatin Drug Interactions Associated with Increased Risk of Myopathy/Rhabdomyolysis
Interacting Agents | Prescribing Recommendations
Cyclosporine | Do not exceed 10 mg atorvastatin daily
Clarithromycin, Itraconazole, HIV protease inhibitors (ritonavir plus saquinavir or lopinavir plus ritonavir,) | Caution when exceeding doses > 20mg atorvastatin daily. The lowest dose necessary should be used.

In patients taking CADUET, therapy should be temporarily withheld or discontinued in any patient with an acute, serious condition suggestive of a myopathy or having a risk factor predisposing to the development of renal failure secondary to rhabdomyolysis (e.g., severe acute infection, hypotension, major surgery, trauma, severe metabolic, endocrine and electrolyte disorders, and uncontrolled seizures).

Liver Dysfunction

Statins, like the atorvastatin component of CADUET and like some other lipid-lowering therapies, have been associated with biochemical abnormalities of liver function. Persistent elevations (>3 times the upper limit of normal [ULN] occurring on 2 or more occasions) in serum transaminases occurred in 0.7% of patients who received atorvastatin in clinical trials. The incidence of these abnormalities was 0.2%, 0.2%, 0.6%, and 2.3% for 10, 20, 40, and 80 mg, respectively.

In clinical trials in patients taking the atorvastatin component of CADUET, the following has been observed. One patient in clinical trials developed jaundice. Increases in liver function tests (LFT) in other patients were not associated with jaundice or other clinical signs or symptoms. Upon dose reduction, drug interruption, or discontinuation, transaminase levels returned to or near pretreatment levels without sequelae. Eighteen of 30 patients, with persistent LFT elevations continued treatment with a reduced dose of atorvastatin.

It is recommended that liver function tests be performed prior to and at 12 weeks following both the initiation of therapy and any elevation of dose, and periodically (e.g., semiannually) thereafter. Liver enzyme changes generally occur in the first 3 months of treatment with the atorvastatin component of CADUET. Patients who develop increased transaminase levels should be monitored until the abnormalities resolve. Should an increase in ALT or AST of >3 times ULN persist, reduction of dose or withdrawal of CADUET is recommended.

Active liver disease or unexplained persistent transaminase elevations are contraindications to the use of CADUET (see CONTRAINDICATIONS).

Increased Angina and/or Myocardial Infarction

Worsening angina and acute myocardial infarction can develop after starting or increasing the dose of amlodipine, particularly in patients with severe obstructive coronary artery disease.

PRECAUTIONS

Hypotension

Symptomatic hypotension is possible, particularly in patients with severe aortic stenosis. Because of the gradual onset of action, acute hypotension is unlikely.

Beta-Blocker Withdrawal

The amlodipine component of CADUET is not a beta-blocker and therefore gives no protection against the dangers of abrupt beta-blocker withdrawal; any such withdrawal should be by gradual reduction of the dose of beta-blocker.

Endocrine Function

Statins, such as the atorvastatin component of CADUET interfere with cholesterol synthesis and theoretically might blunt adrenal and/or gonadal steroid production. Clinical studies have shown that atorvastatin does not reduce basal plasma cortisol concentration or impair adrenal reserve. The effects of statins on male fertility have not been studied in adequate numbers of patients. The effects, if any, on the pituitary-gonadal axis in premenopausal women are unknown. Use caution when administering a statin with drugs that may decrease the levels or activity of endogenous steroid hormones, such as ketoconazole, spironolactone, and cimetidine.

CNS Toxicity Studies with atorvastatin

Brain hemorrhage was seen in a female dog treated with atorvastatin calcium for 3 months at a dose equivalent to 120 mg atorvastatin/kg/day. Brain hemorrhage and optic nerve vacuolation were seen in another female dog that was sacrificed in moribund condition after 11 weeks of escalating doses of atorvastatin calcium equivalent to up to 280 mg atorvastatin/kg/day. The 120 mg/kg dose of atorvastatin resulted in a systemic exposure approximately 16 times the human plasma area-under-the-curve (AUC, 0–24 hours) based on the maximum human dose of 80 mg/day. A single tonic convulsion was seen in each of 2 male dogs (one treated with atorvastatin calcium at a dose equivalent to 10 mg atorvastatin/kg/day and one at a dose equivalent to 120 mg atorvastatin/kg/day) in a 2-year study. No CNS lesions have been observed in mice after chronic treatment for up to 2 years at doses of atorvastatin calcium equivalent to up to 400 mg atorvastatin/kg/day or in rats at doses equivalent to up to 100 mg atorvastatin/kg/day. These doses were 6 to 11 times (mouse) and 8 to 16 times (rat) the human AUC (0–24) based on the maximum recommended human dose of 80 mg atorvastatin/day.

CNS vascular lesions, characterized by perivascular hemorrhages, edema, and mononuclear cell infiltration of perivascular spaces, have been observed in dogs treated with other statins. A chemically similar drug in this class produced optic nerve degeneration (Wallerian degeneration of retinogeniculate fibers) in clinically normal dogs in a dose-dependent fashion at a dose that produced plasma drug levels about 30 times higher than the mean drug level in humans taking the highest recommended dose.

Use in Patients with Recent Stroke or TIAStudies with atorvastatin

In a post-hoc analysis of the Stroke Prevention by Aggressive Reduction in Cholesterol Levels (SPARCL) study where atorvastatin 80 mg vs. placebo was administered in 4,731 subjects without CHD who had a stroke or TIA within the preceding 6 months, a higher incidence of hemorrhagic stroke was seen in the atorvastatin 80 mg group compared to placebo (55, 2.3% atorvastatin vs. 33, 1.4% placebo; HR: 1.68, 95% CI: 1.09, 2.59; p=0.0168). The incidence of fatal hemorrhagic stroke was similar across treatment groups (17 vs. 18 for the atorvastatin and placebo groups, respectively). The incidence of nonfatal hemorrhagic stroke was significantly higher in the atorvastatin group (38, 1.6%) as compared to the placebo group (16, 0.7%). Some baseline characteristics, including hemorrhagic and lacunar stroke on study entry, were associated with a higher incidence of hemorrhagic stroke in the atorvastatin group (see ADVERSE REACTIONS, The Atorvastatin Component of CADUET).

Information for Patients

Because of the risk of myopathy with statins, the drug class to which the atorvastatin component of CADUET belongs, advise patients to promptly report unexplained muscle pain, tenderness, or weakness, particularly if accompanied by malaise or fever.

Drug Interactions

Data from a drug-drug interaction study involving 10 mg of amlodipine and 80 mg of atorvastatin in healthy subjects indicate that the pharmacokinetics of amlodipine are not altered when the drugs are coadministered. The effect of amlodipine on the pharmacokinetics of atorvastatin showed no effect on the Cmax: 91% (90% confidence interval: 80 to 103%), but the AUC of atorvastatin increased by 18% (90% confidence interval: 109 to 127%) in the presence of amlodipine, which was not clinically meaningful.

No drug interaction studies have been conducted with CADUET and other drugs, although studies have been conducted in the individual amlodipine and atorvastatin components, as described below:

Studies with Amlodipine

In vitro data in human plasma indicate that amlodipine has no effect on the protein binding of drugs tested (digoxin, phenytoin, warfarin, and indomethacin).

Cimetidine: Co-administration of amlodipine with cimetidine did not alter the pharmacokinetics of amlodipine.

Maalox® (antacid): Co-administration of the antacid Maalox with a single dose of amlodipine had no significant effect on the pharmacokinetics of amlodipine.

Sildenafil: A single 100 mg dose of sildenafil (Viagra®) in subjects with essential hypertension had no effect on the pharmacokinetic parameters of amlodipine. When amlodipine and sildenafil were used in combination, each agent independently exerted its own blood pressure lowering effect.

Digoxin: Co-administration of amlodipine with digoxin did not change serum digoxin levels or digoxin renal clearance in normal volunteers.

Ethanol (alcohol): Single and multiple 10 mg doses of amlodipine had no significant effect on the pharmacokinetics of ethanol.

Warfarin: Co-administration of amlodipine with warfarin did not change the warfarin prothrombin response time.

In clinical trials, amlodipine has been safely administered with thiazide diuretics, beta-blockers, angiotensin-converting enzyme inhibitors, long-acting nitrates, sublingual nitroglycerin, digoxin, warfarin, non-steroidal anti-inflammatory drugs, antibiotics, and oral hypoglycemic drugs.

Studies with Atorvastatin

The risk of myopathy during treatment with statins is increased with concurrent administration of fibric acid derivatives, lipid-modifying doses of niacin, cyclosporine, or strong CYP 3A4 inhibitors (e.g., clarithromycin, HIV protease inhibitors, and itraconazole) (see WARNINGS, Skeletal Muscle, and CLINICAL PHARMACOLOGY).

Strong Inhibitors of CYP 3A4: Atorvastatin is metabolized by cytochrome P450 3A4. Concomitant administration of atorvastatin with strong inhibitors of CYP 3A4 can lead to increases in plasma concentrations of atorvastatin. The extent of interaction and potentiation of effects depends on the variability of effect on CYP 3A4.

Clarithromycin: Atorvastatin AUC was significantly increased with concomitant administration of atorvastatin 80 mg with clarithromycin (500 mg twice daily) compared to that of atorvastatin alone (see CLINICAL PHARMACOLOGY). Therefore, in patients taking clarithromycin, use caution when administering atorvastatin doses > 20 mg (see WARNINGS, Skeletal Muscle, and DOSAGE AND ADMINISTRATION). Combination of Protease Inhibitors: Atorvastatin AUC was significantly increased with concomitant administration of atorvastatin 40 mg with ritonavir plus saquinavir (400 mg twice daily) or atorvastatin 20 mg with lopinavir plus ritonavir (400 mg + 100 mg twice daily) compared to that of atorvastatin alone (see CLINICAL PHARMACOLOGY). Therefore, in patients taking HIV protease inhibitors, use caution when administering atorvastatin doses ≥20 mg (see WARNINGS, Skeletal Muscle, and DOSAGE AND ADMINISTRATION). Itraconazole: Atorvastatin AUC was significantly increased with concomitant administration of atorvastatin 40 mg and itraconazole 200 mg (see CLINICAL PHARMACOLOGY). Therefore, in patients taking itraconazole, use caution when administering atorvastatin doses ≥20 mg (see WARNINGS, Skeletal Muscle, and DOSAGE AND ADMINISTRATION).

Grapefruit juice: Contains one or more components that inhibit CYP 3A4 and can increase plasma concentrations of atorvastatin, especially with excessive grapefruit juice consumption (>1.2 liters per day).

Cyclosporine: Atorvastatin and atorvastatin-metabolites are substrates of the OATP1B1 transporter. Inhibitors of the OATP1B1 (e.g., cyclosporine) can increase the bioavailability of atorvastatin. Atorvastatin AUC was significantly increased with concomitant administration of atorvastatin 10 mg and cyclosporine 5.2 mg/kg/day compared to that of atorvastatin alone (see CLINICAL PHARMACOLOGY). In cases where coadministration of atorvastatin with cyclosporine is necessary, the dose of atorvastatin should not exceed 10 mg (see WARNINGS, Skeletal Muscle).

Rifampin or other Inducers of Cytochrome P450 3A4: Concomitant administration of atorvastatin with inducers of cytochrome P450 3A4 (e.g., efavirenz, rifampin) can lead to variable reductions in plasma concentrations of atorvastatin. Due to the dual interaction mechanism of rifampin, simultaneous co-administration of atorvastatin with rifampin is recommended, as delayed administration of atorvastatin after administration of rifampin has been associated with a significant reduction in atorvastatin plasma concentrations.

Digoxin: When multiple doses of atorvastatin and digoxin were coadministered, steady-state plasma digoxin concentrations increased by approximately 20%. Patients taking digoxin should be monitored appropriately.

Oral Contraceptives: Coadministration of atorvastatin and an oral contraceptive increased AUC values for norethindrone and ethinyl estradiol (see CLINICAL PHARMACOLOGY). These increases should be considered when selecting an oral contraceptive for a woman taking CADUET.

Warfarin: Atorvastatin had no clinically significant effect on prothrombin time when administered to patients receiving chronic warfarin treatment.

Drug/Laboratory Test Interactions

None known.

Carcinogenesis, Mutagenesis, Impairment of Fertility Studies with amlodipine

Rats and mice treated with amlodipine maleate in the diet for up to two years, at concentrations calculated to provide daily dosage levels of 0.5, 1.25, and 2.5 mg amlodipine/kg/day, showed no evidence of a carcinogenic effect of the drug. For the mouse, the highest dose was, on a mg/m^2 basis, similar to the maximum recommended human dose of 10 mg amlodipine/day1. For the rat, the highest dose level was, on a mg/m^2 basis, about twice the maximum recommended human dose1.

Mutagenicity studies conducted with amlodipine maleate revealed no drug related effects at either the gene or chromosome levels.

There was no effect on the fertility of rats treated orally with amlodipine maleate (males for 64 days and females for 14 days prior to mating) at doses up to 10 mg amlodipine/kg/day (8 times1 the maximum recommended human dose of 10 mg/day on a mg/m^2 basis).

1Based on patent weight of 50 kg. Studies with atorvastatin

In a 2-year carcinogenicity study with atorvastatin calcium in rats at dose levels equivalent to 10, 30, and 100 mg atorvastatin/kg/day, 2 rare tumors were found in muscle in high-dose females: in one, there was a rhabdomyosarcoma and, in another, there was a fibrosarcoma. This dose represents a plasma AUC (0–24) value of approximately 16 times the mean human plasma drug exposure after an 80 mg oral dose.

A 2-year carcinogenicity study in mice given atorvastatin calcium at dose levels equivalent to 100, 200, and 400 mg atorvastatin/kg/day resulted in a significant increase in liver adenomas in high-dose males and liver carcinomas in high-dose females. These findings occurred at plasma AUC (0–24) values of approximately 6 times the mean human plasma drug exposure after an 80 mg oral dose.

In vitro, atorvastatin was not mutagenic or clastogenic in the following tests with and without metabolic activation: the Ames test with Salmonella typhimurium and Escherichia coli, the HGPRT forward mutation assay in Chinese hamster lung cells, and the chromosomal aberration assay in Chinese hamster lung cells. Atorvastatin was negative in the in vivo mouse micronucleus test.

There were no effects on fertility when rats were given atorvastatin calcium at doses equivalent to up to 175 mg atorvastatin/kg/day (15 times the human exposure). There was aplasia and aspermia in the epididymides of 2 of 10 rats treated with atorvastatin calcium at a dose equivalent to 100 mg atorvastatin/kg/day for 3 months (16 times the human AUC at the 80 mg dose); testis weights were significantly lower at 30 and 100 mg/kg/day and epididymal weight was lower at 100 mg/kg/day. Male rats given the equivalent of 100 mg atorvastatin/kg/day for 11 weeks prior to mating had decreased sperm motility, spermatid head concentration, and increased abnormal sperm. Atorvastatin caused no adverse effects on semen parameters, or reproductive organ histopathology in dogs given doses of atorvastatin calcium equivalent to 10, 40, or 120 mg atorvastatin/kg/day for two years.

Pregnancy Pregnancy Category X

(see CONTRAINDICATIONS)

CADUET contains atorvastatin and is therefore contraindicated in women who are pregnant or may become pregnant. The atorvastatin component of CADUET may cause fetal harm when administered to a pregnant woman. CADUET should be administered to women of child-bearing potential only when such patients are highly unlikely to conceive and have been informed of the potential hazards. If the woman becomes pregnant while taking CADUET, it should be discontinued immediately and the patient advised again as to the potential hazards to the fetus, and the lack of known clinical benefit with continued use during pregnancy.

Serum cholesterol and triglycerides increase during normal pregnancy, and cholesterol products are essential for fetal development. Atherosclerosis is a chronic process, and discontinuation of lipid-lowering drugs during pregnancy should have little impact on long-term outcomes of primary hypercholesterolemia therapy.

Studies with amlodipine

No evidence of teratogenicity or other embryo/fetal toxicity was found when pregnant rats and rabbits were treated orally with amlodipine maleate at doses up to 10 mg amlodipine/kg/day (respectively 8 times1 and 23 times1 the maximum recommended human dose of 10 mg/day on a mg/m^2 basis) during their respective periods of major organogenesis. However, litter size was significantly decreased (by about 50%) and the number of intrauterine deaths was significantly increased (about 5-fold) in rats receiving amlodipine maleate at 10 mg amlodipine/kg/day for 14 days before mating and throughout mating and gestation. Amlodipine maleate has been shown to prolong both the gestation period and the duration of labor in rats at this dose. There are no adequate and well-controlled studies in pregnant women.

Studies with atorvastatin

There are no adequate and well-controlled studies of atorvastatin use during pregnancy. There have been rare reports of congenital anomalies following intrauterine exposure to statins. In a review of about 100 prospectively followed pregnancies in women exposed to other statins, the incidences of congenital anomalies, spontaneous abortions, and fetal deaths/stillbirths did not exceed the rate expected in the general population. However, this study was only able to exclude a three-to-four-fold increased risk of congenital anomalies over background incidence. In 89% of these cases, drug treatment started before pregnancy and stopped during the first trimester when pregnancy was identified.

Atorvastatin crosses the rat placenta and reaches a level in fetal liver equivalent to that of maternal plasma. Atorvastatin was not teratogenic in rats at doses of atorvastatin calcium equivalent to up to 300 mg atorvastatin/kg/day or in rabbits at doses of atorvastatin calcium equivalent to up to 100 mg atorvastatin/kg/day. These doses resulted in multiples of about 30 times (rat) or 20 times (rabbit) the human exposure based on surface area (mg/m^2).

In a study in rats given atorvastatin calcium at doses equivalent to 20, 100, or 225 mg atorvastatin/kg/day, from gestation day 7 through to lactation day 21 (weaning), there was decreased pup survival at birth, neonate, weaning, and maturity for pups of mothers dosed with 225 mg/kg/day. Body weight was decreased on days 4 and 21 for pups of mothers dosed at 100 mg/kg/day; pup body weight was decreased at birth and at days 4, 21, and 91 at 225 mg/kg/day. Pup development was delayed (rotorod performance at 100 mg/kg/day and acoustic startle at 225 mg/kg/day; pinnae detachment and eye opening at 225 mg/kg/day). These doses of atorvastatin correspond to 6 times (100 mg/kg) and 22 times (225 mg/kg) the human AUC at 80 mg/day.

Labor and Delivery

No studies have been conducted in pregnant women on the effect of CADUET, amlodipine or atorvastatin on the mother or the fetus during labor or delivery, or on the duration of labor or delivery. Amlodipine has been shown to prolong the duration of labor in rats.

Nursing Mothers Studies with amlodipine

It is not known whether the amlodipine component of CADUET is excreted in human milk.

Studies with atorvastatin

It is not known whether the atorvastatin component of CADUET is excreted in human milk, but a small amount of another drug in this class does pass into breast milk. Nursing rat pups taking atorvastatin had plasma and liver drug levels of 50% and 40%, respectively, of that in their mother's milk. Animal breast milk drug levels may not accurately reflect human breast milk levels. Because another drug in this class passes into human milk and because statins have a potential to cause serious adverse reactions in nursing infants, women taking CADUET, which includes atorvastatin, should be advised not to nurse their infants (see CONTRAINDICATIONS).

Pediatric Use

There have been no studies conducted to determine the safety or effectiveness of CADUET in pediatric populations.

Studies with amlodipine

The effect of amlodipine on blood pressure in patients less than 6 years of age is not known.

Studies with atorvastatin

Safety and effectiveness in patients 10–17 years of age with heterozygous familial hypercholesterolemia have been evaluated in controlled clinical trials of 6 months duration in adolescent boys and postmenarchal girls. Patients treated with atorvastatin had an adverse experience profile generally similar to that of patients treated with placebo, the most common adverse experiences observed in both groups, regardless of causality assessment, were infections. Doses greater than 20 mg have not been studied in this patient population. In this limited controlled study, there was no significant effect on growth or sexual maturation in boys or on menstrual cycle length in girls. See CLINICAL PHARMACOLOGY, Clinical Studies section; ADVERSE REACTIONS, Pediatric Patients; and DOSAGE AND ADMINISTRATION, Pediatric Patients (10–17 years of age) with Heterozygous Familial Hypercholesterolemia. Adolescent females should be counseled on appropriate contraceptive methods while on atorvastatin therapy (see CONTRAINDICATIONS and PRECAUTIONS, Pregnancy). Atorvastatin has not been studied in controlled clinical trials involving pre-pubertal patients or patients younger than 10 years of age.

Clinical efficacy with doses of atorvastatin up to 80 mg/day for 1 year have been evaluated in an uncontrolled study of patients with homozygous FH including 8 pediatric patients. See CLINICAL PHARMACOLOGY, Clinical Studies, Atorvastatin Effects in Homozygous Familial Hypercholesterolemia.

Geriatric Use

There have been no studies conducted to determine the safety or effectiveness of CADUET in geriatric populations.

In studies with amlodipine

Clinical studies of amlodipine did not include sufficient numbers of subjects aged 65 and over to determine whether they respond differently from younger subjects. Other reported clinical experience has not identified differences in responses between the elderly and younger patients. In general, dose selection of the amlodipine component of CADUET for an elderly patient should be cautious, usually starting at the low end of the dosing range, reflecting the greater frequency of decreased hepatic, renal, or cardiac function, and of concomitant disease or other drug therapy. Elderly patients have decreased clearance of amlodipine with a resulting increase of AUC of approximately 40–60%, and a lower initial dose may be required (see DOSAGE AND ADMINISTRATION).

In studies with atorvastatin

Of the 39,828 patients who received LIPITOR in clinical studies, 15,813 (40%) were ≥65 years old and 2,800 (7%) were ≥75 years old. No overall differences in safety or effectiveness were observed between these subjects and younger subjects, and other reported clinical experience has not identified differences in responses between the elderly and younger patients, but greater sensitivity of some older adults cannot be ruled out. Advanced age (≥65 years) is a predisposing factor for myopathy.

ADVERSE REACTIONS

CADUET

CADUET (amlodipine besylate/atorvastatin calcium) has been evaluated for safety in 1092 patients in double-blind placebo controlled studies treated for co-morbid hypertension and dyslipidemia. In general, treatment with CADUET was well tolerated. For the most part, adverse experiences have been mild or moderate in severity. In clinical trials with CADUET, no adverse experiences peculiar to this combination have been observed. Adverse experiences are similar in terms of nature, severity, and frequency to those reported previously with amlodipine and atorvastatin.

The following information is based on the clinical experience with amlodipine and atorvastatin.

The Amlodipine Component of CADUET

Amlodipine has been evaluated for safety in more than 11,000 patients in U.S. and foreign clinical trials. In general, treatment with amlodipine was well tolerated at doses up to 10 mg daily. Most adverse reactions reported during therapy with amlodipine were of mild or moderate severity. In controlled clinical trials directly comparing amlodipine (N=1730) in doses up to 10 mg to placebo (N=1250), discontinuation of amlodipine due to adverse reactions was required in only about 1.5% of patients and was not significantly different from placebo (about 1%). The most common side effects are headache and edema. The incidence (%) of side effects which occurred in a dose related manner are as follows:

Adverse Event | amlodipine
 | 2.5 mg N=275 | 5.0 mg N=296 | 10.0 mg N=268 | Placebo N=520
Edema | 1.8 | 3.0 | 10.8 | 0.6
Dizziness | 1.1 | 3.4 | 3.4 | 1.5
Flushing | 0.7 | 1.4 | 2.6 | 0.0
Palpitations | 0.7 | 1.4 | 4.5 | 0.6

Other adverse experiences which were not clearly dose related but which were reported with an incidence greater than 1.0% in placebo-controlled clinical trials include the following:

Placebo-Controlled Studies

Adverse Event | amlodipine (%) (N=1730) | Placebo (%) (N=1250)
Headache | 7.3 | 7.8
Fatigue | 4.5 | 2.8
Nausea | 2.9 | 1.9
Abdominal Pain | 1.6 | 0.3
Somnolence | 1.4 | 0.6

For several adverse experiences that appear to be drug and dose related, there was a greater incidence in women than men associated with amlodipine treatment as shown in the following table:

Adverse Event | amlodipine |  | Placebo
 | M=% (N=1218) | F=% (N=512) | M=% (N=914) | F=% (N=336)
Edema | 5.6 | 14.6 | 1.4 | 5.1
Flushing | 1.5 | 4.5 | 0.3 | 0.9
Palpitations | 1.4 | 3.3 | 0.9 | 0.9
Somnolence | 1.3 | 1.6 | 0.8 | 0.3

The following events occurred in ≤1% but >0.1% of patients treated with amlodipine in controlled clinical trials or under conditions of open trials or marketing experience where a causal relationship is uncertain; they are listed to alert the physician to a possible relationship:

Cardiovascular: arrhythmia (including ventricular tachycardia and atrial fibrillation), bradycardia, chest pain, hypotension, peripheral ischemia, syncope, tachycardia, postural dizziness, postural hypotension, vasculitis.

Central and Peripheral Nervous System: hypoesthesia, neuropathy peripheral, paresthesia, tremor, vertigo.

Gastrointestinal: anorexia, constipation, dyspepsia,2 dysphagia, diarrhea, flatulence, pancreatitis, vomiting, gingival hyperplasia.

General: allergic reaction, asthenia,2 back pain, hot flushes, malaise, pain, rigors, weight gain, weight decrease.

Musculoskeletal System: arthralgia, arthrosis, muscle cramps,2 myalgia.

Psychiatric: sexual dysfunction (male2 and female), insomnia, nervousness, depression, abnormal dreams, anxiety, depersonalization.

Respiratory System: dyspnea,2 epistaxis.

Skin and Appendages: angioedema, erythema multiforme, pruritus,2 rash,2 rash erythematous, rash maculopapular.

Special Senses: abnormal vision, conjunctivitis, diplopia, eye pain, tinnitus.

Urinary System: micturition frequency, micturition disorder, nocturia.

Autonomic Nervous System: dry mouth, sweating increased.

Metabolic and Nutritional: hyperglycemia, thirst.

Hemopoietic: leukopenia, purpura, thrombocytopenia.

The following events occurred in ≤0.1% of patients treated with amlodipine in controlled clinical trials or under conditions of open trials or marketing experience: cardiac failure, pulse irregularity, extrasystoles, skin discoloration, urticaria, skin dryness, alopecia, dermatitis, muscle weakness, twitching, ataxia, hypertonia, migraine, cold and clammy skin, apathy, agitation, amnesia, gastritis, increased appetite, loose stools, coughing, rhinitis, dysuria, polyuria, parosmia, taste perversion, abnormal visual accommodation, and xerophthalmia.

Other reactions occurred sporadically and cannot be distinguished from medications or concurrent disease states such as myocardial infarction and angina.

Amlodipine therapy has not been associated with clinically significant changes in routine laboratory tests. No clinically relevant changes were noted in serum potassium, serum glucose, total triglycerides, total cholesterol, HDL cholesterol, uric acid, blood urea nitrogen, or creatinine.

In the CAMELOT and PREVENT studies (see CLINICAL PHARMACOLOGY Clinical Studies, Clinical Studies with Amlodipine) the adverse event profile was similar to that reported previously (see above), with the most common adverse event being peripheral edema.

The following postmarketing event has been reported infrequently with amlodipine treatment where a causal relationship is uncertain: gynecomastia. In postmarketing experience, jaundice and hepatic enzyme elevations (mostly consistent with cholestasis or hepatitis) in some cases severe enough to require hospitalization have been reported in association with use of amlodipine.

Amlodipine has been used safely in patients with chronic obstructive pulmonary disease, well-compensated congestive heart failure, peripheral vascular disease, diabetes mellitus, and abnormal lipid profiles.

2These events occurred in less than 1% in placebo-controlled trials, but the incidence of these side effects was between 1% and 2% in all multiple dose studies. The Atorvastatin Component of CADUET

The following serious adverse reactions are discussed in greater detail in other sections of the label:
Rhabdomyolysis and myopathy (see WARNINGS, Skeletal Muscle)
Liver enzyme abnormalities (see WARNINGS, Liver Dysfunction)

Clinical Adverse Experiences

Because clinical trials are conducted under widely varying conditions, the adverse reaction rates observed in the clinical studies of a drug cannot be directly compared to rates in the clinical trials of another drug and may not reflect the rates observed in clinical practice.

In the LIPITOR placebo-controlled clinical trial database of 16,066 patients (8755 LIPITOR vs. 7311 placebo; age range 10–93 years, 39% women, 91% Caucasians, 3% Blacks, 2% Asians, 4% other) with a median treatment duration of 53 weeks, 9.7% of patients on LIPITOR and 9.5% of the patients on placebo discontinued due to adverse reactions regardless of causality. The five most common adverse reactions in patients treated with LIPITOR that led to treatment discontinuation and occurred at a rate greater than placebo were: myalgia (0.7%), diarrhea (0.5%), nausea (0.4%), alanine aminotransferase increase (0.4%), and hepatic enzyme increase (0.4%).

The most commonly reported adverse reactions (incidence ≥ 2% and greater than placebo) regardless of causality, in patients treated with LIPITOR in placebo controlled trials (n=8755) were: nasopharyngitis (8.3%), arthralgia (6.9%), diarrhea (6.8%), pain in extremity (6.0%), and urinary tract infection (5.7%).

Table 13 summarizes the frequency of clinical adverse reactions, regardless of causality, reported in ≥ 2% and at a rate greater than placebo in patients treated with LIPITOR (n=8755), from seventeen placebo-controlled trials.

Table 13. Clinical adverse reactions occurring in ≥ 2% in patents treated with any dose of LIPITOR and at an incidence greater than placebo regardless of causality (% of patients).
Adverse Reaction* | Any dose N=8755 | 10 mg N=3908 | 20 mg N=188 | 40 mg N=604 | 80 mg N=4055 | Placebo N=7311
Nasopharyngitis | 8.3 | 12.9 | 5.3 | 7.0 | 4.2 | 8.2
Arthralgia | 6.9 | 8.9 | 11.7 | 10.6 | 4.3 | 6.5
Diarrhea | 6.8 | 7.3 | 6.4 | 14.1 | 5.2 | 6.3
Pain in extremity | 6.0 | 8.5 | 3.7 | 9.3 | 3.1 | 5.9
Urinary tract infection | 5.7 | 6.9 | 6.4 | 8.0 | 4.1 | 5.6
Dyspepsia | 4.7 | 5.9 | 3.2 | 6.0 | 3.3 | 4.3
Nausea | 4.0 | 3.7 | 3.7 | 7.1 | 3.8 | 3.5
Musculoskeletal pain | 3.8 | 5.2 | 3.2 | 5.1 | 2.3 | 3.6
Muscle Spasm | 3.6 | 4.6 | 4.8 | 5.1 | 2.4 | 3.0
Myalgia | 3.5 | 3.6 | 5.9 | 8.4 | 2.7 | 3.1
Insomnia | 3.0 | 2.8 | 1.1 | 5.3 | 2.8 | 2.9
Pharyngolaryngeal pain | 2.3 | 3.9 | 1.6 | 2.8 | 0.7 | 2.1

* Adverse Reaction greater than or equal to 2% in any dose greater than placebo

Other adverse reactions reported in placebo-controlled studies include:
Body as a whole: malaise, pyrexia; Digestive system: abdominal discomfort, eructation, flatulence, hepatitis, cholestasis; Musculoskeletal system: musculoskeletal pain, muscle fatigue, neck pain, joint swelling; Metabolic and nutritional system: transaminases increase, liver function test abnormal, blood alkaline phosphatase increase, creatine phosphokinase increase, hyperglycemia; Nervous system: nightmare; Respiratory system: epistaxis; Skin and appendages: urticaria; Special senses: vision blurred, tinnitus; Urogenital system: white blood cells urine positive.

Anglo-Scandinavian Cardiac Outcomes Trial (ASCOT)

In ASCOT (see CLINICAL PHARMACOLOGY, Clinical Studies, Clinical Studies with Atorvastatin) involving 10,305 participants (age range 40–80 years, 19% women; 94.6% Caucasians, 2.6% Africans, 1.5% South Asians, 1.3% mixed/other) treated with atorvastatin 10 mg daily (n=5,168) or placebo (n=5,137), the safety and tolerability profile of the group treated with atorvastatin was comparable to that of the group treated with placebo during a median of 3.3 years of follow-up.

Collaborative Atorvastatin Diabetes Study (CARDS)

In CARDS (see CLINICAL PHARMACOLOGY, Clinical Studies, Clinical Studies with Atorvastatin) involving 2838 subjects (age range 39–77 years, 32% women; 94.3% Caucasians, 2.4% South Asians, 2.3% Afro-Caribbean, 1.0% other)with type 2 diabetes treated with LIPITOR 10 mg daily (n=1428) or placebo (n=1410), there was no difference in the overall frequency of adverse reactions or serious adverse reactions between the treatment groups during a median follow-up of 3.9 years. No cases of rhabdomyolysis were reported.

Treating to New Targets Study (TNT)

In TNT (see CLINICAL PHARMACOLOGY, Clinical Studies) involving 10,001 subjects (age range 29–78 years, 19% women; 94.1% Caucasians, 2.9% Blacks, 1.0% Asians, 2.0% other) with clinically evident CHD treated with LIPITOR 10 mg daily (n=5006) or LIPITOR 80 mg daily (n=4995), there were more serious adverse reactions and discontinuations due to adverse reactions in the high-dose atorvastatin group (92, 1.8%; 497, 9.9%, respectively) as compared to the low-dose group (69, 1.4%; 404, 8.1%, respectively) during a median follow-up of 4.9 years. Persistent transaminase elevations (≥3 × ULN twice within 4–10 days) occurred in 62 (1.3%) individuals with atorvastatin 80 mg and in nine (0.2%) individuals with atorvastatin 10 mg. Elevations of CK (≥ 10 × ULN) were low overall, but were higher in the high-dose atorvastatin treatment group (13, 0.3%) compared to the low-dose atorvastatin group (6, 0.1%).

Incremental Decrease in Endpoints Through Aggressive Lipid Lowering Study (IDEAL)

In IDEAL (see CLINICAL PHARMACOLOGY, Clinical Studies) involving 8,888 subjects (age range 26–80 years, 19% women; 99.3% Caucasians, 0.4% Asians, 0.3% Blacks, 0.04% other) treated with LIPITOR 80 mg/day (n=4439) or simvastatin 20–40 mg daily (n=4449), there was no difference in the overall frequency of adverse reactions or serious adverse reactions between the treatment groups during a median follow-up of 4.8 years.

Stroke Prevention by Aggressive Reduction in Cholesterol Levels (SPARCL)

In SPARCL involving 4731 subjects (age range 21–92 years, 40% women; 93.3% Caucasians, 3.0% Blacks, 0.6% Asians, 3.1% other) without clinically evident CHD but with a stroke or transient ischemic attack (TIA) within the previous 6 months treated with LIPITOR 80 mg (n=2365) or placebo (n=2366) for a median follow-up of 4.9 years, there was a higher incidence of persistent hepatic transaminase elevations (≥ 3 × ULN twice within 4–10 days) in the atorvastatin group (0.9%) compared to placebo (0.1%). Elevations of CK (>10 × ULN) were rare, but were higher in the atorvastatin group (0.1%) compared to placebo (0.0%). Diabetes was reported as an adverse reaction in 144 subjects (6.1%) in the atorvastatin group and 89 subjects (3.8%) in the placebo group (see PRECAUTIONS).

In a post-hoc analysis, LIPITOR 80 mg reduced the incidence of ischemic stroke (218/2365, 9.2% vs. 274/2366, 11.6%) and increased the incidence of hemorrhagic stroke (55/2365, 2.3% vs. 33/2366, 1.4%) compared to placebo. The incidence of fatal hemorrhagic stroke was similar between groups (17 LIPITOR vs. 18 placebo). The incidence of non-fatal hemorrhagic strokes was significantly greater in the atorvastatin group (38 non-fatal hemorrhagic strokes) as compared to the placebo group (16 non-fatal hemorrhagic strokes). Subjects who entered the study with a hemorrhagic stroke appeared to be at increased risk for hemorrhagic stroke [7 (16%) LIPITOR vs. 2 (4%) placebo].

There were no significant differences between the treatment groups for all-cause mortality: 216 (9.1%) in the LIPITOR 80 mg/day group vs. 211 (8.9%) in the placebo group. The proportions of subjects who experienced cardiovascular death were numerically smaller in the LIPITOR 80 mg group (3.3%) than in the placebo group (4.1%). The proportions of subjects who experienced non-cardiovascular death were numerically larger in the LIPITOR 80 mg group (5.0%) than in the placebo group (4.0%).

Postintroduction Reports with Atorvastatin

The following adverse reactions have been identified during postapproval use of the atorvastatin component of CADUET. Because these reactions are reported voluntarily from a population of uncertain size, it is not always possible to reliably estimate their frequency or establish a causal relationship to drug exposure.

Adverse reactions associated with atorvastatin therapy reported since market introduction, that are not listed above, regardless of causality assessment, include the following: anaphylaxis, angioneurotic edema, bullous rashes (including erythema multiforme, Stevens-Johnson syndrome, and toxic epidermal necrolysis), rhabdomyolysis, fatigue, tendon rupture, hepatic failure, dizziness, memory impairment, depression, and peripheral neuropathy.

Pediatric Patients (ages 10–17 years)

In a 26-week controlled study in boys and postmenarchal girls (n=140, 31% female; 92% Caucasians, 1.6% Blacks, 1.6% Asians, 4.8% other), the safety and tolerability profile of atorvastatin 10 to 20 mg daily was generally similar to that of placebo (see CLINICAL PHARMACOLOGY, Clinical Studies section and PRECAUTIONS, Pediatric Use).

OVERDOSAGE

There is no information on overdosage with CADUET in humans.

Information on Amlodipine

Single oral doses of amlodipine maleate equivalent to 40 mg amlodipine/kg and 100 mg amlodipine/kg in mice and rats, respectively, caused deaths. Single oral amlodipine maleate doses equivalent to 4 or more mg amlodipine/kg in dogs (11 or more times the maximum recommended clinical dose on a mg/m^2 basis) caused a marked peripheral vasodilation and hypotension.

Overdosage might be expected to cause excessive peripheral vasodilation with marked hypotension and possibly a reflex tachycardia. In humans, experience with intentional overdosage of amlodipine is limited. Reports of intentional overdosage include a patient who ingested 250 mg and was asymptomatic and was not hospitalized; another (120 mg) was hospitalized, underwent gastric lavage and remained normotensive; the third (105 mg) was hospitalized and had hypotension (90/50 mmHg) which normalized following plasma expansion. A patient who took 70 mg amlodipine and an unknown quantity of benzodiazepine in a suicide attempt developed shock which was refractory to treatment and died the following day with abnormally high benzodiazepine plasma concentration. A case of accidental drug overdose has been documented in a 19-month-old male who ingested 30 mg amlodipine (about 2 mg/kg). During the emergency room presentation, vital signs were stable with no evidence of hypotension, but a heart rate of 180 bpm. Ipecac was administered 3.5 hours after ingestion and on subsequent observation (overnight) no sequelae were noted.

If overdose should occur, begin active cardiac and respiratory monitoring. Perform frequent blood pressure measurements. Should hypotension occur, initiate cardiovascular support including elevation of the extremities and administration of fluids. If hypotension remains unresponsive to these conservative measures, consider administration of vasopressors (such as phenylephrine) with specific attention to circulating volume and urine output. As amlodipine is highly protein bound, hemodialysis is not likely to be of benefit.

Information on Atorvastatin

There is no specific treatment for atorvastatin overdosage. In the event of an overdose, the patient should be treated symptomatically, and supportive measures instituted as required. Due to extensive drug binding to plasma proteins, hemodialysis is not expected to significantly enhance atorvastatin clearance.

DOSAGE AND ADMINISTRATION

Dosage of CADUET must be individualized on the basis of both effectiveness and tolerance for each individual component in the treatment of hypertension/angina and hyperlipidemia.

Amlodipine (Hypertension or angina) Adults

The usual initial antihypertensive oral dose of amlodipine is 5 mg once daily with a maximum dose of 10 mg once daily. Small, fragile, or elderly individuals, or patients with hepatic insufficiency may be started on 2.5 mg once daily and this dose may be used when adding amlodipine to other antihypertensive therapy.

Dosage should be adjusted according to each patient's need. In general, titration should proceed over 7 to 14 days so that the physician can fully assess the patient's response to each dose level. Titration may proceed more rapidly, however, if clinically warranted, provided the patient is assessed frequently.

The recommended dose of amlodipine for chronic stable or vasospastic angina is 5–10 mg, with the lower dose suggested in the elderly and in patients with hepatic insufficiency. Most patients will require 10 mg for adequate effect. See ADVERSE REACTIONS section for information related to dosage and side effects.

The recommended dose range of amlodipine for patients with coronary artery disease is 5–10 mg once daily. In clinical studies the majority of patients required 10 mg (see CLINICAL PHARMACOLOGY, Clinical studies).

Children

The effective antihypertensive oral dose of amlodipine in pediatric patients ages 6–17 years is 2.5 mg to 5 mg once daily. Doses in excess of 5 mg daily have not been studied in pediatric patients (see CLINICAL PHARMACOLOGY).

Atorvastatin (Hyperlipidemia) Hyperlipidemia (Heterozygous Familial and Nonfamilial) and Mixed Dyslipidemia (Fredrickson Types IIa and IIb)

The recommended starting dose of atorvastatin is 10 or 20 mg once daily. Patients who require a large reduction in LDL-C (more than 45%) may be started at 40 mg once daily. The dosage range of atorvastatin is 10 to 80 mg once daily. Atorvastatin can be administered as a single dose at any time of the day, with or without food. The starting dose and maintenance doses of atorvastatin should be individualized according to patient characteristics such as goal of therapy and response (see current NCEP Guidelines). After initiation and/or upon titration of atorvastatin, lipid levels should be analyzed within 2 to 4 weeks and dosage adjusted accordingly.

Heterozygous Familial Hypercholesterolemia in Pediatric Patients (10–17 years of age)

The recommended starting dose of atorvastatin is 10 mg/day; the maximum recommended dose is 20 mg/day (doses greater than 20 mg have not been studied in this patient population). Doses should be individualized according to the recommended goal of therapy (see current NCEP Pediatric Panel Guidelines3, CLINICAL PHARMACOLOGY, and INDICATIONS AND USAGE). Adjustments should be made at intervals of 4 weeks or more.

3National Cholesterol Education Program (NCEP): Highlights of the Report of the Expert Panel on Blood Cholesterol Levels in Children Adolescents. Pediatrics. 89(3):495–501. 1992. Homozygous Familial Hypercholesterolemia

The dosage of atorvastatin in patients with homozygous FH is 10 to 80 mg daily. Atorvastatin should be used as an adjunct to other lipid-lowering treatments (e.g., LDL apheresis) in these patients or if such treatments are unavailable. Note: a 2.5/80 mg CADUET tablet is not available. Management of patients needing a 2.5/80 mg combination requires individual assessments of dyslipidemia and therapy with the individual components as a 2.5/80 mg CADUET tablet is not available.

Concomitant Lipid Lowering Therapy

Atorvastatin may be used with bile acid resins. Monitor for signs of myopathy in patients receiving the combination of statins and fibrates (see WARNINGS, Skeletal Muscle, and PRECAUTIONS, Drug Interactions).

Dosage in Patients With Renal Impairment

Renal disease does not affect the plasma concentrations nor LDL-C reduction of atorvastatin; thus, dosage adjustment in patients with renal dysfunction is not necessary (see WARNINGS, Skeletal Muscle, and CLINICAL PHARMACOLOGY, Specific Populations).

Dosage in Patients Taking Cyclosporine, Clarithromycin, Itraconazole, or a Combination of Ritonavir plus Saquinavir or Lopinavir plus Ritonavir

In patients taking cyclosporine, therapy should be limited to LIPITOR 10 mg once daily. In patients taking clarithromycin, itraconazole or in patients with HIV taking a combination of ritonavir plus saquinavir or lopinavir plus ritonavir, for doses of atorvastatin exceeding 20 mg, appropriate clinical assessment is recommended to ensure that the lowest dose necessary of atorvastatin is employed (see WARNINGS, Skeletal Muscle, and PRECAUTIONS, Drug Interactions).

CADUET

CADUET may be substituted for its individually titrated components. Patients may be given the equivalent dose of CADUET or a dose of CADUET with increased amounts of amlodipine, atorvastatin or both for additional antianginal effects, blood pressure lowering, or lipid lowering effect.

CADUET may be used to provide additional therapy for patients already on one of its components. As initial therapy for one indication and continuation of treatment of the other, the recommended starting dose of CADUET should be selected based on the continuation of the component being used and the recommended starting dose for the added monotherapy.

CADUET may be used to initiate treatment in patients with hyperlipidemia and either hypertension or angina. The recommended starting dose of CADUET should be based on the appropriate combination of recommendations for the monotherapies. The maximum dose of the amlodipine component of CADUET is 10 mg once daily. The maximum dose of the atorvastatin component of CADUET is 80 mg once daily.

See above for detailed information related to the dosing and administration of amlodipine and atorvastatin.

HOW SUPPLIED

CADUET tablets contain amlodipine besylate and atorvastatin calcium equivalent to amlodipine and atorvastatin in the dose strengths described below.

CADUET tablets are differentiated by tablet color/size and are engraved with "Pfizer" on one side and a unique number on the other side. CADUET tablets are supplied for oral administration in the following strengths and package configurations:

Table 14. CADUET Packaging Configurations
CADUET
Package Configuration | Tablet Strength (amlodipine besylate/ atorvastatin calcium) mg | NDC # | Engraving | Tablet Color
Bottle of 30 | 2.5/20 | 54868-5672-0 | CDT 252 | White
Bottle of 30 | 2.5/40 | 54868-5699-0 | CDT 254 | White
Bottle of 30 Bottle of 90 | 5/10 | 54868-3287-0 54868-3287-1 | CDT 051 | White
Bottle of 30 Bottle of 90 | 5/20 | 54868-1207-0 54868-1207-1 | CDT 052 | White
Bottle of 30 | 5/40 | 54868-5179-0 | CDT 054 | White
Bottle of 30 | 5/80 | 54868-5420-0 | CDT 058 | White
Bottle of 30 | 10/10 | 54868-5567-0 | CDT 101 | Blue
Bottle of 30 Bottle of 90 | 10/20 | 54868-5209-0 54868-5209-1 | CDT 102 | Blue
Bottle of 30 Bottle of 90 | 10/40 | 54868-5200-0 54868-5200-1 | CDT 104 | Blue
Bottle of 30 Bottle of 90 | 10/80 | 54868-5523-0 54868-5523-1 | CDT 108 | Blue

Store at 25°C (77°F); excursions permitted to 15–30°C (59–86°F) [see USP Controlled Room Temperature].

Rx only

Manufactured by:
Pfizer Ireland Pharmaceuticals
Dublin, Ireland

LAB-0276-15.0

January 2010

PATIENT INFORMATION

Read the patient information that comes with CADUET before you start taking it, and each time you get a refill. There may be new information. This information does not replace talking with your doctor about your condition or treatment. If you have any questions about CADUET, ask your doctor or pharmacist.

What is CADUET?

CADUET is a prescription drug that combines Norvasc® (amlodipine besylate) and Lipitor® (atorvastatin calcium) in one pill.

CADUET is used in adults who need both Norvasc and Lipitor.

Norvasc is used to treat:

- High blood pressure (hypertension) and
- Chest pain (angina) and
- Blocked arteries of the heart (coronary artery disease)

Lipitor is used to lower the levels of "bad" cholesterol and triglycerides in your blood. It can also raise the levels of "good" cholesterol.

Lipitor is also used to lower the risk for heart attack, stroke, certain types of heart surgery, and chest pain in patients who have heart disease or risk factors for heart disease such as:

- age, smoking, high blood pressure, low HDL-C, heart disease in the family

Lipitor can lower the risk for heart attack or stroke in patients with diabetes and risk factors such as:

- diabetic eye or kidney problems, smoking, or high blood pressure.

CADUET has not been studied in children.

Who should not use CADUET?

Do not use CADUET if you:

- Are pregnant or think you may be pregnant, or are planning to become pregnant. CADUET may harm your unborn baby. If you get pregnant, stop taking CADUET and call your doctor right away.
- Are breastfeeding. CADUET can pass into your breast milk and may harm your baby. Do not breastfeed if you take CADUET.
- Have liver problems.
- Are allergic to anything in CADUET. The active ingredients are atorvastatin calcium and amlodipine besylate. See the end of this leaflet for a complete list of ingredients.

What should I tell my doctor before taking CADUET?

Tell your doctor about all of your health conditions, including, if you have:

- heart disease
- muscle aches or weakness
- diabetes
- thyroid problems
- kidney problems
- or drink more than 2 glasses of alcohol daily

Tell your doctor about all the medicines you take including prescription and nonprescription medicines, vitamins and herbal supplements. CADUET and some other medicines can interact, causing serious side effects. Especially tell your doctor if you take medicines for:

- your immune system
- infections
- cholesterol
- birth control
- heart failure
- HIV (AIDS)

You can use nitroglycerin and CADUET together. If you take nitroglycerin for chest pain (angina), do not stop taking it while taking CADUET.

Know all the medicines you take. Keep a list of them with you to show your doctor and pharmacist.

How should I take CADUET?

- Take CADUET once a day, exactly as your doctor tells you. Do not change your dose or stop CADUET without talking to your doctor.
- Take CADUET each day at any time of day, at about the same time each day. CADUET can be taken with or without food.
- Do not break the tablets before taking them. Talk to your doctor if you have a problem swallowing pills.
- Your doctor should start you on a low-fat diet before giving you CADUET. Stay on this low-fat diet when you take CADUET.
- CADUET comes in many different strengths. Your doctor will test your cholesterol and blood pressure to find the right dose for you.
- If you miss a dose, take it as soon as you remember. Do not take CADUET if it has been more than 12 hours since your missed dose. Just take the next dose at your regular time. Do not take 2 doses of CADUET at the same time.
- If too much CADUET is taken by accident, call your doctor or poison control center, or go to the nearest emergency room.

What should I avoid while taking CADUET?

- Avoid getting pregnant. If you get pregnant, stop taking CADUET right away and call your doctor.
- Do not breastfeed. CADUET can pass into your breast milk and may harm your baby.

What are possible side effects of CADUET?

CADUET can cause serious side effects. These side effects happen only to a small number of people. Your doctor can monitor you for them. These side effects usually go away if your dose is lowered or CADUET is stopped. These serious side effects include:

- Muscle problems. CADUET can cause serious muscle problems that can lead to kidney problems, including kidney failure. You have a higher chance for muscle problems if you are taking certain other medicines with CADUET.
- Liver problems. CADUET can cause liver problems. Your doctor may do blood tests to check your liver before you start taking CADUET and while you take it.

Call your doctor right away if:

- you have muscle problems like weakness, tenderness, or pain that happen without a good reason, especially if you also have a fever or feel more tired than usual
- allergic reactions including swelling of the face, lips, tongue, and/or throat that may cause difficulty in breathing or swallowing which may require treatment right away.
- you have nausea and vomiting, stomach pain
- you are passing brown or dark-colored urine
- you feel more tired than usual
- your skin and white of your eyes get yellow
- allergic skin reactions.

- Chest pain that does not go away or gets worse. Sometimes, when you start CADUET or increase your dose, chest pain can get worse or a heart attack can happen. If this happens, call your doctor or go to the emergency room right away.

Common side effects of CADUET include:

- headache
- tiredness
- stomach pain
- upset stomach
- swelling of your legs or ankles (edema)
- hot or warm feeling in your face (flushing)
- irregular heartbeat (arrhythmia)
- very fast heartbeat (heart palpitations)
- muscle and joint pain
- alterations in some laboratory blood tests
- dizziness
- extreme sleepiness
- nausea
- diarrhea

Additional side effects have been reported: tendon problems.

Talk to your doctor or pharmacist about side effects that bother you or do not go away.

There are other side effects of CADUET. Ask your doctor or pharmacist for a complete list.

How do I store CADUET?

- Store CADUET at room temperature, 68 to 77°F (20 to 25°C).
- Do not keep medicine that is out-of-date or that you no longer need.
- Keep CADUET and all medicines out of the reach of children. Keep medicines in places where children cannot get it.

General information about CADUET

Medicines are sometimes prescribed for conditions that are not mentioned in patient information leaflets. Do not use CADUET for a condition for which it was not prescribed. Do not give CADUET to other people, even if they have the same problem you have. It may harm them.

This leaflet summarizes the most important information about CADUET. If you want more information, talk with your doctor. Ask your doctor or pharmacist for information about CADUET written for health professionals. You can also go to the CADUET website at www.CADUET.com, or call 866-514-0900.

What is high blood pressure (hypertension)?

You have high blood pressure when the force of blood against the walls of your arteries stays high. This can damage your heart and other parts of your body. Drugs that lower blood pressure lower your risk of having a stroke or heart attack.

What is angina (chest pain)?

Angina is a pain that keeps coming back when part of your heart does not get enough blood. It feels like something is pressing or squeezing your chest under the breastbone. Sometimes you can feel it in your shoulders, arms, neck, jaw, or back.

What is cholesterol?

Cholesterol is a fat-like substance made in your body. It is also found in foods. You need some cholesterol for good health, but too much is not good for you. Cholesterol can clog your blood vessels.

What is a heart attack?

A heart attack occurs when heart muscle does not get enough blood. Symptoms include chest pain, trouble breathing, nausea, and weakness. Heart muscle cells may be damaged or die. The heart cannot pump well or may stop beating.

What is a stroke?

A stroke occurs when nerve cells in the brain do not get enough blood. The cells may be damaged or die. The damaged cells may cause weakness or problems speaking or thinking.

WHAT ARE THE INGREDIENTS IN CADUET?

Active ingredients: amlodipine besylate, atorvastatin calcium

Inactive ingredients: calcium carbonate, croscarmellose sodium, microcrystalline cellulose, pregelatinized starch, polysorbate 80, hydroxypropyl cellulose, purified water, colloidal silicon dioxide (anhydrous), magnesium stearate

Film coating: Opadry® II White 85F28751 (polyvinyl alcohol, titanium dioxide, PEG 3000 and talc) or Opadry® II Blue 85F10919 (polyvinyl alcohol, titanium dioxide, PEG 3000, talc, and FD&C blue #2)

Rx only

Manufactured by Pfizer Ireland Pharmaceuticals
Dublin, Ireland

LAB-0347-3.0
July 2009

PRINCIPAL DISPLAY PANEL

Caduet ®
(amlodipine besylate /
atorvastatin calcium)

2.5 mg/20 mg*

Caduet ®
(amlodipine besylate /
atorvastatin calcium)

2.5 mg/40 mg*

Caduet ®
(amlodipine besylate /
atorvastatin calcium)

5 mg/10 mg*

Caduet ®
(amlodipine besylate /
atorvastatin calcium)

5 mg/20 mg*

Caduet ®
(amlodipine besylate /
atorvastatin calcium)

5 mg/40 mg*

Caduet ®
(amlodipine besylate /
atorvastatin calcium)

5 mg/80 mg*

Caduet ®
(amlodipine besylate /
atorvastatin calcium)

10 mg/10 mg*

Caduet ®
(amlodipine besylate /
atorvastatin calcium)

10 mg/20 mg*

Caduet ®
(amlodipine besylate /
atorvastatin calcium)

10 mg/40 mg*

Caduet ®
(amlodipine besylate /
atorvastatin calcium)

10 mg/80 mg*